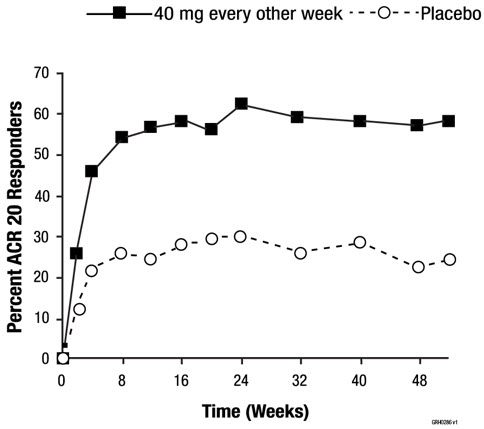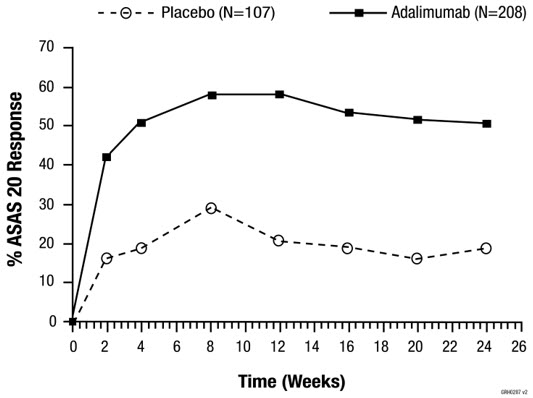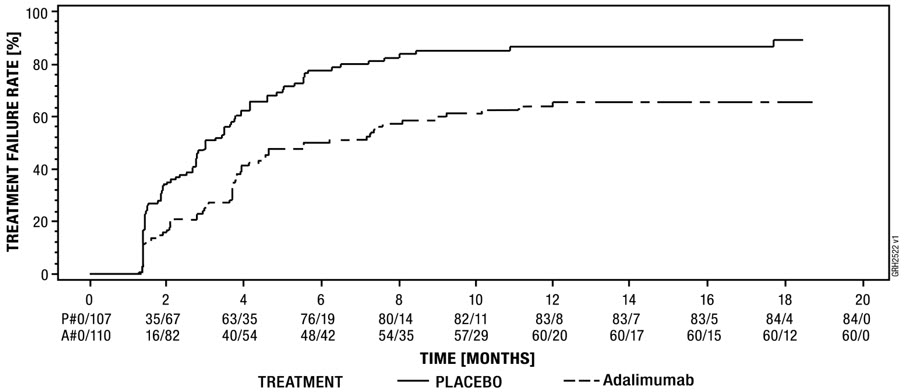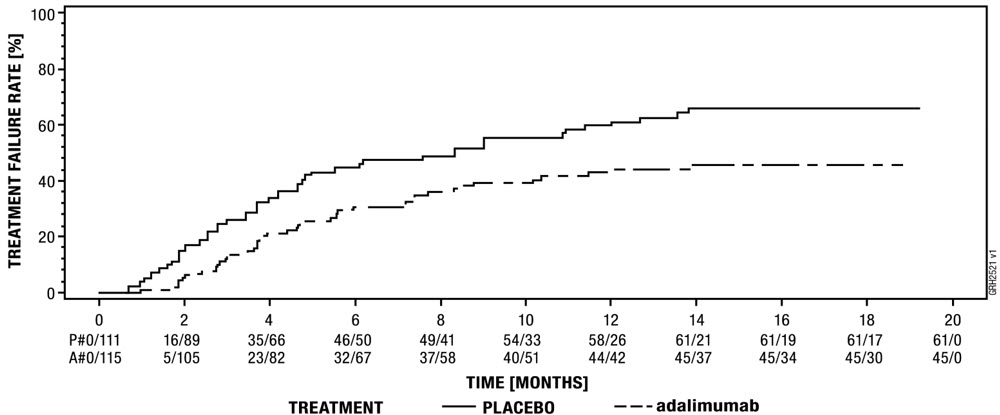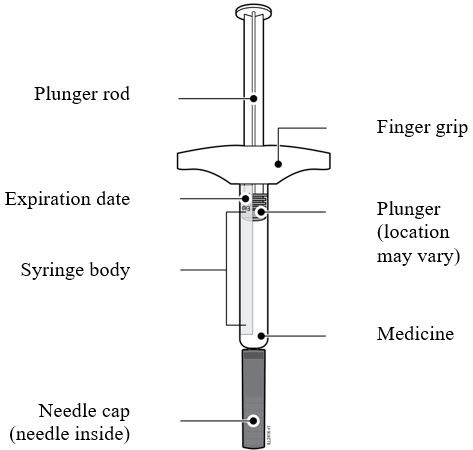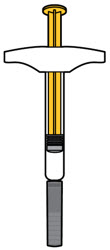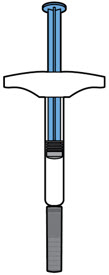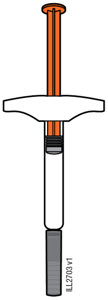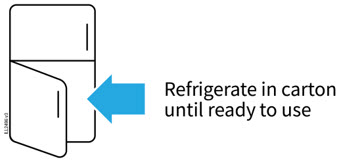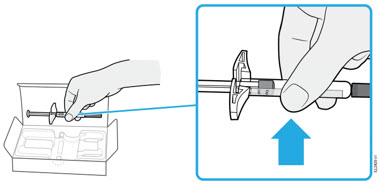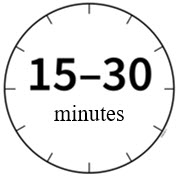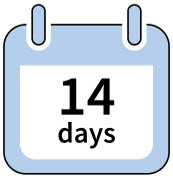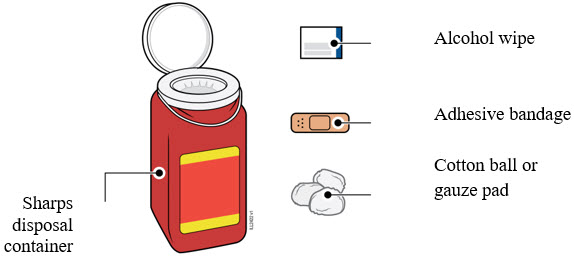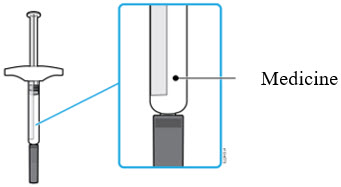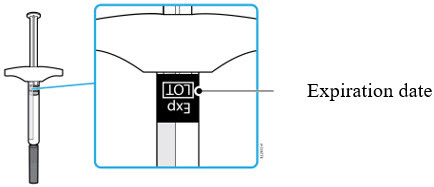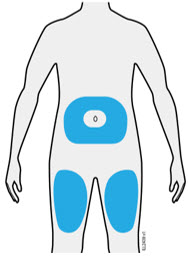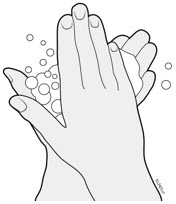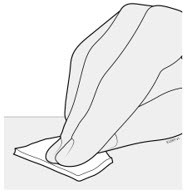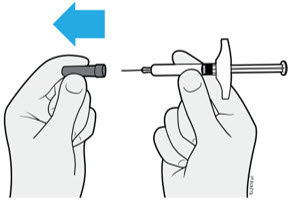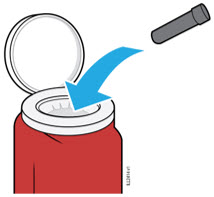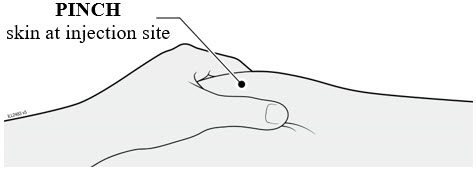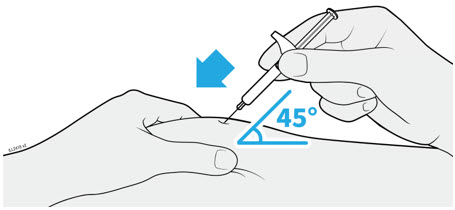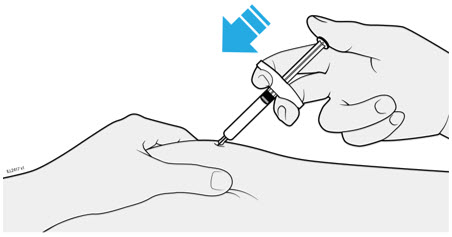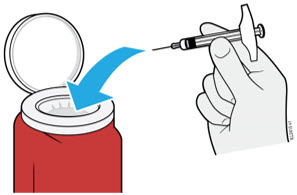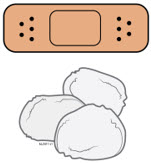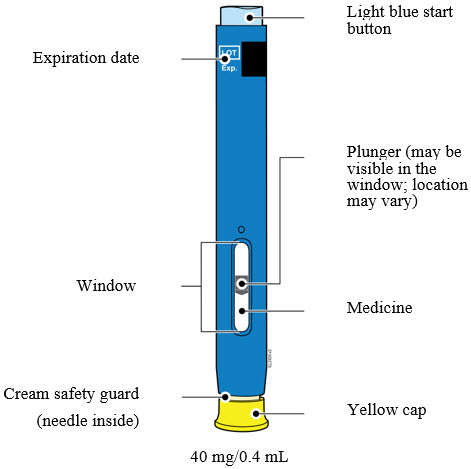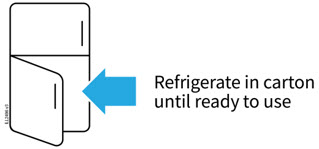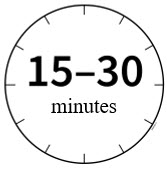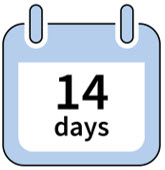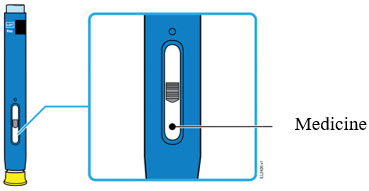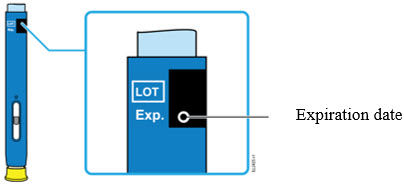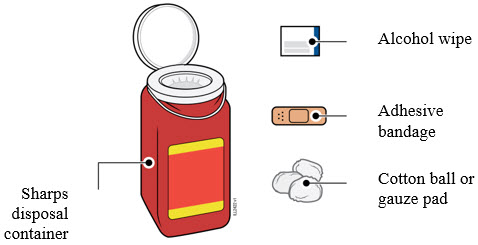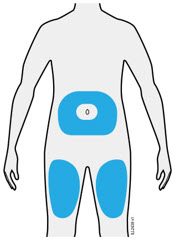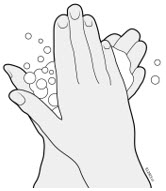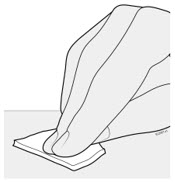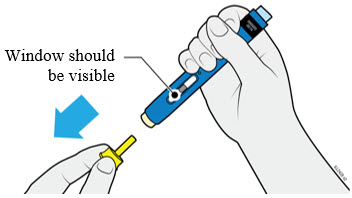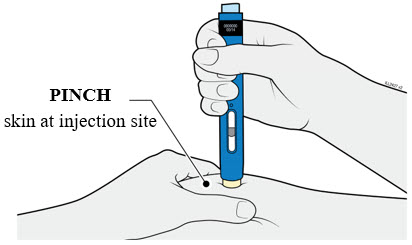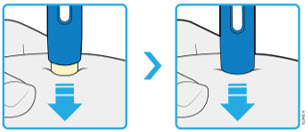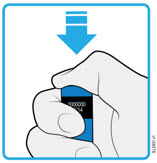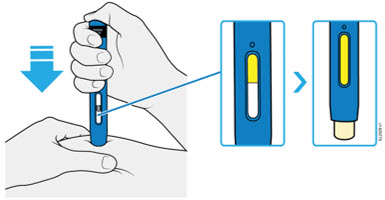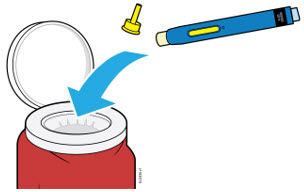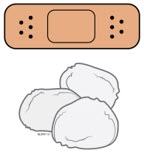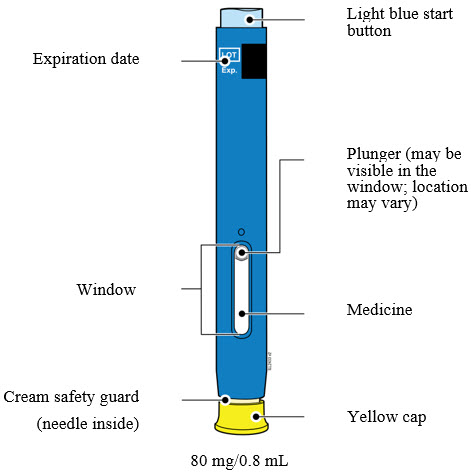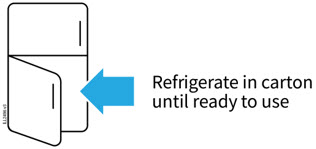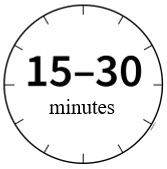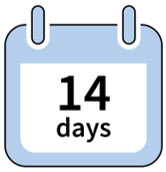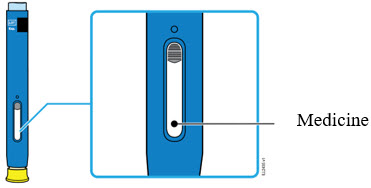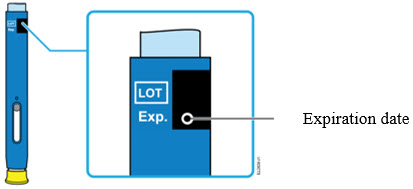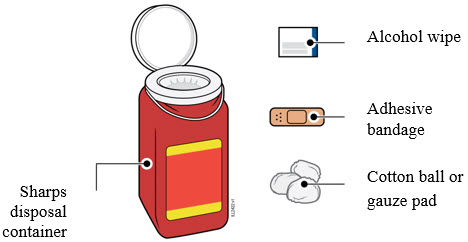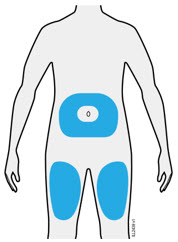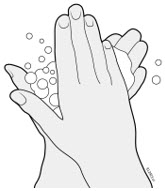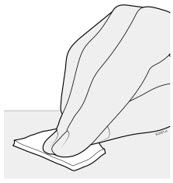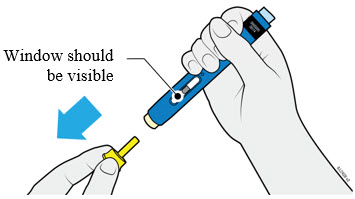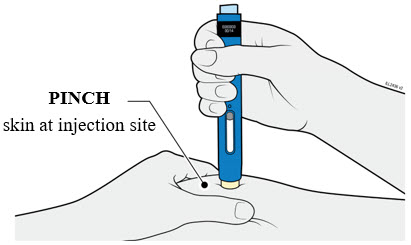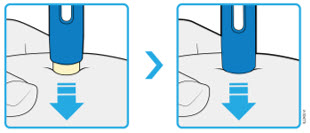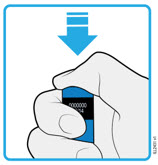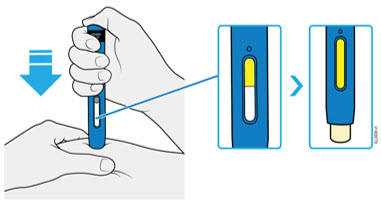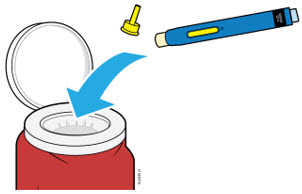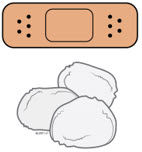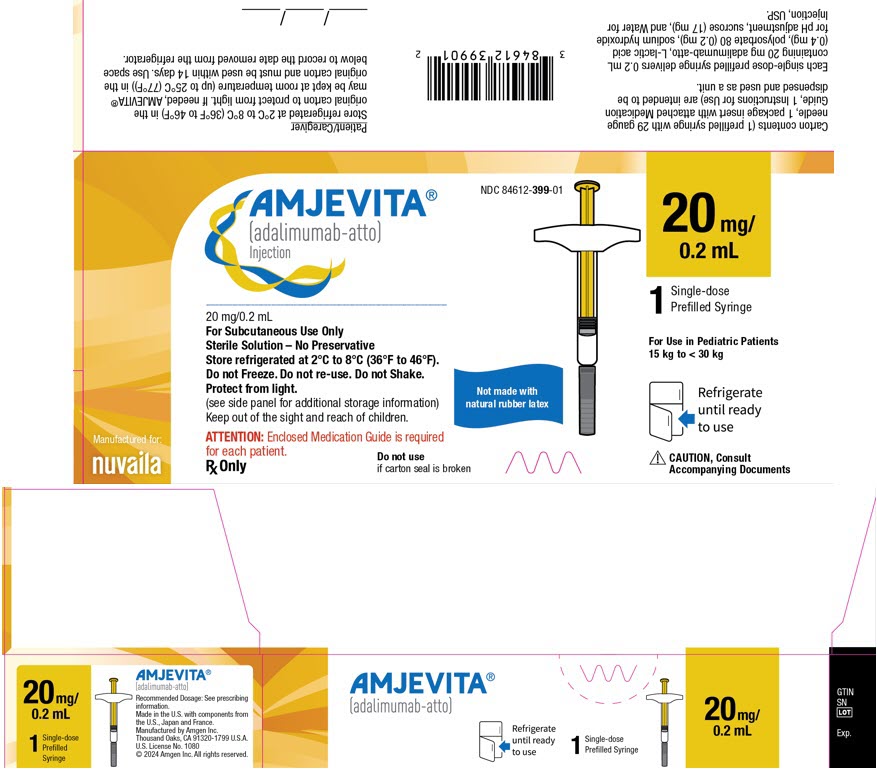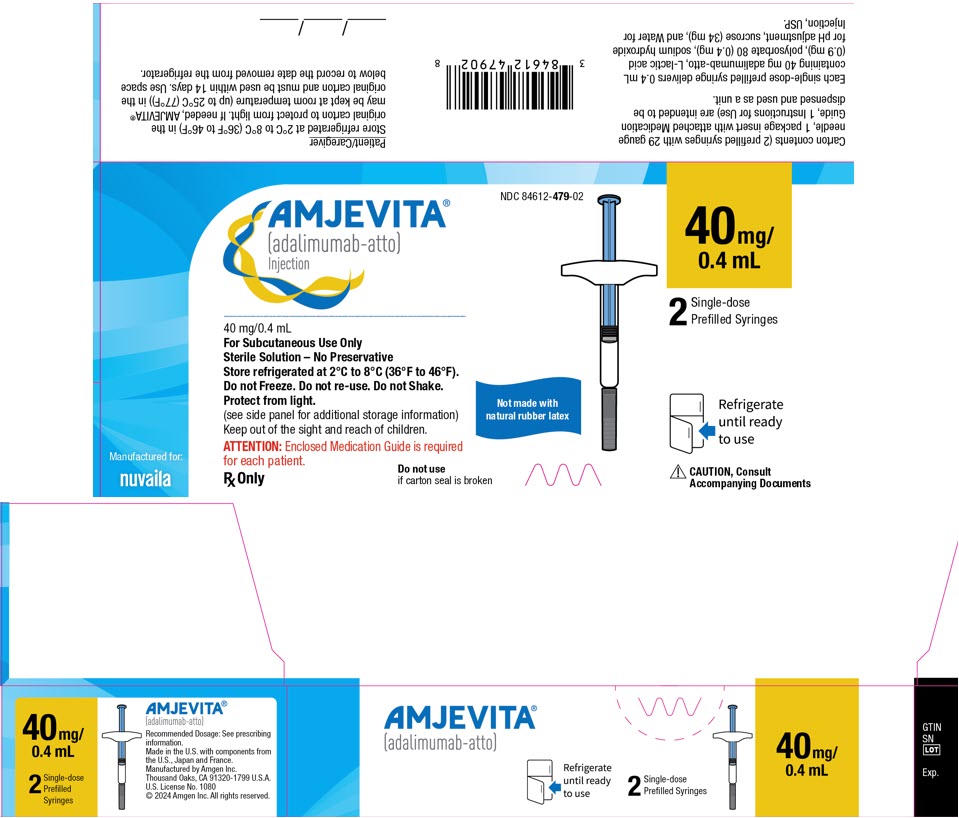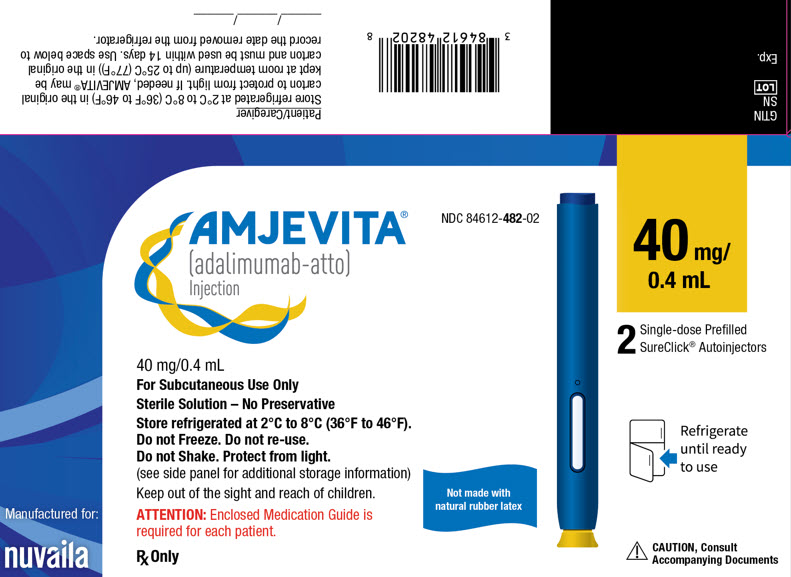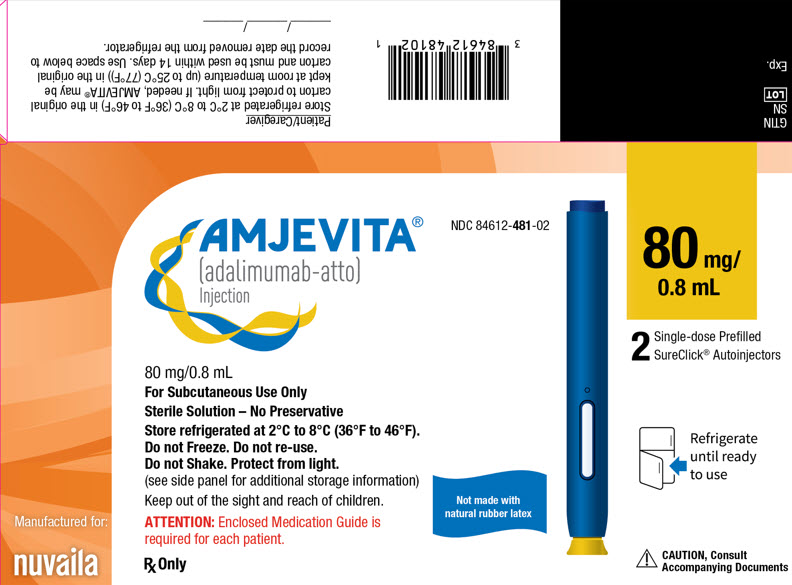 DRUG LABEL: AMJEVITA
NDC: 84612-399 | Form: INJECTION
Manufacturer: Nuvaila Limited
Category: prescription | Type: HUMAN PRESCRIPTION DRUG LABEL
Date: 20260126

ACTIVE INGREDIENTS: ADALIMUMAB 20 mg/0.2 mL
INACTIVE INGREDIENTS: SUCROSE 17 mg/0.2 mL; POLYSORBATE 80 0.2 mg/0.2 mL; ACETIC ACID 0.4 mg/0.2 mL; SODIUM HYDROXIDE; WATER

HIGHLIGHTS OF PRESCRIBING INFORMATION

These highlights do not include all the information needed to use AMJEVITA safely and effectively. See full prescribing information for AMJEVITA.
AMJEVITA (adalimumab-atto) injection, for subcutaneous use
Initial U.S. Approval: 2016
AMJEVITA (adalimumab-atto) is biosimilar to HUMIRA (adalimumab).

WARNING: SERIOUS INFECTIONS and MALIGNANCY

See full prescribing information for complete boxed warning.

SERIOUS INFECTIONS (5.1, 6.1):

- Increased risk of serious infections leading to hospitalization or death, including tuberculosis (TB), bacterial sepsis, invasive fungal infections (such as histoplasmosis), and infections due to other opportunistic pathogens.
- Discontinue AMJEVITA if a patient develops a serious infection or sepsis during treatment.
- Perform test for latent TB; if positive, start treatment for TB prior to starting AMJEVITA.
- Monitor all patients for active TB during treatment, even if initial latent TB test is negative.

MALIGNANCY (5.2):

- Lymphoma and other malignancies, some fatal, have been reported in children and adolescent patients treated with TNF-blockers including adalimumab products.
- Post-marketing cases of hepatosplenic T-cell lymphoma (HSTCL), a rare type of T-cell lymphoma, have occurred in adolescent and young adults with inflammatory bowel disease treated with TNF-blockers including adalimumab products.

1 INDICATIONS AND USAGE

AMJEVITA is a tumor necrosis factor (TNF) blocker indicated for:

- Rheumatoid Arthritis (RA) (1.1): reducing signs and symptoms, inducing major clinical response, inhibiting the progression of structural damage, and improving physical function in adult patients with moderately to severely active RA.
- Juvenile Idiopathic Arthritis (JIA) (1.2): reducing signs and symptoms of moderately to severely active polyarticular JIA in patients 2 years of age and older.
- Psoriatic Arthritis (PsA) (1.3): reducing signs and symptoms, inhibiting the progression of structural damage, and improving physical function in adult patients with active PsA.
- Ankylosing Spondylitis (AS) (1.4): reducing signs and symptoms in adult patients with active AS.
- Crohn's Disease (CD) (1.5): treatment of moderately to severely active Crohn's disease in adults and pediatric patients 6 years of age and older .
- Ulcerative Colitis (UC) (1.6): treatment of moderately to severely active ulcerative colitis in adult patients.
  Limitations of Use:Effectiveness has not been established in patients who have lost response to or were intolerant to TNF-blockers.
- Plaque Psoriasis (Ps) (1.7): treatment of adult patients with moderate to severe chronic plaque psoriasis who are candidates for systemic therapy or phototherapy, and when other systemic therapies are medically less appropriate.
- Hidradenitis Suppurativa (HS) (1.8) : treatment of moderate to severe hidradenitis suppurativa in adult patients.
- Uveitis (UV) (1.9): treatment of non-infectious intermediate, posterior, and panuveitis in adult patients.

2 DOSAGE AND ADMINISTRATION

- Administer by subcutaneous injection (2)
  Rheumatoid Arthritis, Psoriatic Arthritis, Ankylosing Spondylitis (2.1):
- Adults:40 mg every other week.
  - Some patients with RA not receiving methotrexate may benefit from increasing the dosage to 40 mg every week or 80 mg every other week.

Juvenile Idiopathic Arthritis (2.2):

Pediatric Weight 2 Years of Age and Older | Recommended Dosage
15 kg (33 lbs) to less than 30 kg (66 lbs) | 20 mg every other week
30 kg (66 lbs) and greater | 40 mg every other week

Crohn's Disease (2.3):

- Adults:160 mg on Day 1 (given in one day or split over two consecutive days); 80 mg on Day 15; and 40 mg every other week starting on Day 29.
- Pediatric Patients 6 Years of Age and Older:

Pediatric Weight | Recommended Dosage
Pediatric Weight | Days 1 and 15 | Starting on Day 29
17 kg (37 lbs) to less than 40 kg (88 lbs) | Day 1: 80 mg Day 15: 40 mg | 20 mg every other week
40 kg (88 lbs) and greater | Day 1: 160 mg (single-dose or split over two consecutive days) Day 15: 80 mg | 40 mg every other week

Ulcerative Colitis (2.4):

- Adults:160 mg on Day 1 (given in one day or split over two consecutive days), 80 mg on Day 15 and 40 mg every other week starting on Day 29. Discontinue in patients without evidence of clinical remission by eight weeks (Day 57).

Plaque Psoriasis or Adult Uveitis (2.5):

- Adults:80 mg initial dose, followed by 40 mg every other week starting one week after initial dose.

Hidradenitis Suppurativa (2.6)

- Adults:
  - Day 1:160 mg (given in one day or split over two consecutive days)
  - Day 15: 80 mg
  - Day 29 and subsequent doses: 40 mg every week or 80 mg every other week

3 DOSAGE FORMS AND STRENGTHS

Injection:

- Single-dose prefilled SureClick®autoinjector: 80 mg/0.8 mL, 40 mg/0.4 mL (3)
- Single-dose prefilled glass syringe: 80 mg/0.8 mL, 40 mg/0.4 mL, 20 mg/0.2 mL (3)

4 CONTRAINDICATIONS

None (4)

5 WARNINGS AND PRECAUTIONS

- Serious infections:Do not start AMJEVITA during an active infection. If an infection develops, monitor carefully, and stop AMJEVITA if infection becomes serious. (5.1)
- Invasive fungal infections:For patients who develop a systemic illness on AMJEVITA, consider empiric antifungal therapy for those who reside or travel to regions where mycoses are endemic. (5.1)
- Malignancies:Incidence of malignancies was greater in adalimumab-treated patients than in controls. (5.2)
- Anaphylaxis or serious hypersensitivity reactionsmay occur. (5.3)
- Hepatitis B virus reactivation:Monitor HBV carriers during and several months after therapy. If reactivation occurs, stop AMJEVITA and begin anti-viral therapy. (5.4)
- Demyelinating disease:Exacerbation or new onset, may occur. (5.5)
- Cytopenias, pancytopenia:Advise patients to seek immediate medical attention if symptoms develop, and consider stopping AMJEVITA. (5.6)
- Heart failure:Worsening or new onset, may occur. (5.8)
- Lupus-like syndrome:Stop AMJEVITA if syndrome develops. (5.9)

6 ADVERSE REACTIONS

Most common adverse reactions (> 10%): infections (e.g., upper respiratory, sinusitis), injection site reactions, headache and rash (6.1)

To report SUSPECTED ADVERSE REACTIONS, contact Amgen Medical Information at 1-800-77-AMGEN (1-800-772-6436) or FDA at 1-800-FDA-1088 or www.fda.gov/medwatch

7 DRUG INTERACTIONS

- Abatacept:Increased risk of serious infection (5.1, 5.11, 7.2)
- Anakinra:Increased risk of serious infection (5.1, 5.7, 7.2)
- Live vaccines:Avoid use with AMJEVITA (5.10, 7.3)

FULL PRESCRIBING INFORMATION

WARNING: SERIOUS INFECTIONS and MALIGNANCY

SERIOUS INFECTIONS

Patients treated with adalimumab products including AMJEVITA are at increased risk for developing serious infections that may lead to hospitalization or death [see Warnings and Precautions (5.1)] . Most patients who developed these infections were taking concomitant immunosuppressants such as methotrexate or corticosteroids.

Discontinue AMJEVITA if a patient develops a serious infection or sepsis.

Reported infections include:

- Active tuberculosis (TB), including reactivation of latent TB. Patients with TB have frequently presented with disseminated or extrapulmonary disease. Test patients for latent TB before AMJEVITA use and during therapy. Initiate treatment for latent TB prior to AMJEVITA use.
- Invasive fungal infections, including histoplasmosis, coccidioidomycosis, candidiasis, aspergillosis, blastomycosis, and pneumocystosis. Patients with histoplasmosis or other invasive fungal infections may present with disseminated, rather than localized, disease. Antigen and antibody testing for histoplasmosis may be negative in some patients with active infection. Consider empiric anti-fungal therapy in patients at risk for invasive fungal infections who develop severe systemic illness.
- Bacterial, viral and other infections due to opportunistic pathogens, including Legionella and Listeria.

Carefully consider the risks and benefits of treatment with AMJEVITA prior to initiating therapy in patients with chronic or recurrent infection.

Monitor patients closely for the development of signs and symptoms of infection during and after treatment with AMJEVITA, including the possible development of TB in patients who tested negative for latent TB infection prior to initiating therapy [see Warnings and Precautions (5.1)and Adverse Reactions (6.1)].

MALIGNANCY

Lymphoma and other malignancies, some fatal, have been reported in children and adolescent patients treated with TNF-blockers including adalimumab products [see Warnings and Precautions (5.2)]. Post-marketing cases of hepatosplenic T-cell lymphoma (HSTCL), a rare type of T-cell lymphoma, have been reported in patients treated with TNF-blockers including adalimumab products. These cases have had a very aggressive disease course and have been fatal. The majority of reported TNF-blocker cases have occurred in patients with Crohn's disease or ulcerative colitis and the majority were in adolescent and young adult males. Almost all these patients had received treatment with azathioprine or 6-mercaptopurine (6–MP) concomitantly with a TNF-blocker at or prior to diagnosis. It is uncertain whether the occurrence of HSTCL is related to use of a TNF-blocker or a TNF-blocker in combination with these other immunosuppressants [see Warnings and Precautions (5.2)].

1 INDICATIONS AND USAGE

1.1 Rheumatoid Arthritis

AMJEVITA is indicated for reducing signs and symptoms, inducing major clinical response, inhibiting the progression of structural damage, and improving physical function in adult patients with moderately to severely active rheumatoid arthritis. AMJEVITA can be used alone or in combination with methotrexate or other non-biologic disease-modifying anti-rheumatic drugs (DMARDs).

1.2 Juvenile Idiopathic Arthritis

AMJEVITA is indicated for reducing signs and symptoms of moderately to severely active polyarticular juvenile idiopathic arthritis in patients 2 years of age and older. AMJEVITA can be used alone or in combination with methotrexate.

1.3 Psoriatic Arthritis

AMJEVITA is indicated for reducing signs and symptoms, inhibiting the progression of structural damage, and improving physical function in adult patients with active psoriatic arthritis.

AMJEVITA can be used alone or in combination with non-biologic DMARDs.

1.4 Ankylosing Spondylitis

AMJEVITA is indicated for reducing signs and symptoms in adult patients with active ankylosing spondylitis.

1.5 Crohn's Disease

AMJEVITA is indicated for the treatment of moderately to severely active Crohn's disease in adults and pediatric patients 6 years of age and older.

1.6 Ulcerative Colitis

AMJEVITA is indicated for the treatment of moderately to severely active ulcerative colitis in adult patients.

Limitations of Use

The effectiveness of adalimumab products has not been established in patients who have lost response to or were intolerant to TNF-blockers [see Clinical Studies (14.7)] .

1.7 Plaque Psoriasis

AMJEVITA is indicated for the treatment of adult patients with moderate to severe chronic plaque psoriasis who are candidates for systemic therapy or phototherapy, and when other systemic therapies are medically less appropriate. AMJEVITA should only be administered to patients who will be closely monitored and have regular follow-up visits with a physician [see Boxed Warningand Warnings and Precautions (5)] .

1.8 Hidradenitis Suppurativa

AMJEVITA is indicated for the treatment of moderate to severe hidradenitis suppurativa in adult patients.

1.9 Uveitis

AMJEVITA is indicated for the treatment of non-infectious intermediate, posterior, and panuveitis in adult patients.

2 DOSAGE AND ADMINISTRATION

2.1 Rheumatoid Arthritis, Psoriatic Arthritis, and Ankylosing Spondylitis

The recommended subcutaneous dosage of AMJEVITA for adult patients with rheumatoid arthritis (RA), psoriatic arthritis (PsA), or ankylosing spondylitis (AS) is 40 mg administered every other week. Methotrexate (MTX), other non-biologic DMARDs, glucocorticoids, nonsteroidal anti-inflammatory drugs (NSAIDs), and/or analgesics may be continued during treatment with AMJEVITA. In the treatment of RA, some patients not taking concomitant MTX may derive additional benefit from increasing the dosage of AMJEVITA to 40 mg every week or 80 mg every other week.

2.2 Juvenile Idiopathic Arthritis

The recommended subcutaneous dosage of AMJEVITA for patients 2 years of age and older with polyarticular juvenile idiopathic arthritis (JIA) is based on weight as shown below. MTX, glucocorticoids, NSAIDs, and/or analgesics may be continued during treatment with AMJEVITA.

Pediatric Weight (2 Years of Age and Older) | Recommended Dosage
15 kg (33 lbs) to less than 30 kg (66 lbs) | 20 mg every other week
30 kg (66 lbs) and greater | 40 mg every other week

Adalimumab products have not been studied in patients with polyarticular JIA less than 2 years of age or in patients with a weight below 10 kg.

2.3 Crohn's Disease

Adults

The recommended subcutaneous dosage of AMJEVITA for adult patients with Crohn's disease (CD) is 160 mg initially on Day 1 (given in one day or split over two consecutive days), followed by 80 mg two weeks later (Day 15). Two weeks later (Day 29) begin a dosage of 40 mg every other week. Aminosalicylates and/or corticosteroids may be continued during treatment with AMJEVITA. Azathioprine, 6-mercaptopurine (6-MP) [see Warnings and Precautions (5.2)] or MTX may be continued during treatment with AMJEVITA if necessary.

Pediatrics

The recommended subcutaneous dosage of AMJEVITA for pediatric patients 6 years of age and older with Crohn's disease (CD) is based on body weight as shown below:

Pediatric Weight | Recommended Dosage
Pediatric Weight | Days 1 through 15 | Starting on Day 29
17 kg (37 lbs) to less than 40 kg (88 lbs) | Day 1: 80 mg Day 15: 40 mg | 20 mg every other week
40 kg (88 lbs) and greater | Day 1: 160 mg (single dose or split over two consecutive days) Day 15: 80 mg | 40 mg every other week

2.4 Ulcerative Colitis

Adults

The recommended subcutaneous dosage of AMJEVITA for adult patients with UC is 160 mg initially on Day 1 (given in one day or split over two consecutive days), followed by 80 mg two weeks later (Day 15). Two weeks later (Day 29) continue with a dosage of 40 mg every other week.

Discontinue AMJEVITA in adult patients without evidence of clinical remission by eight weeks (Day 57) of therapy. Aminosalicylates and/or corticosteroids may be continued during treatment with AMJEVITA. Azathioprine and 6-mercaptopurine (6-MP) [see Warnings and Precautions (5.2)] may be continued during treatment with AMJEVITA if necessary.

2.5 Plaque Psoriasis or Adult Uveitis

The recommended subcutaneous dosage of AMJEVITA for adult patients with plaque psoriasis (Ps) or Uveitis (UV) is an initial dose of 80 mg, followed by 40 mg given every other week starting one week after the initial dose. The use of adalimumab products in moderate to severe chronic Ps beyond one year has not been evaluated in controlled clinical studies.

2.6 Hidradenitis Suppurativa

Adults

The recommended subcutaneous dosage of AMJEVITA for adult patients with hidradenitis suppurativa (HS) is an initial dose of 160 mg (given in one day or split over two consecutive days), followed by 80 mg two weeks later (Day 15). Begin 40 mg weekly or 80 mg every other week dosing two weeks later (Day 29).

2.7 Monitoring to Assess Safety

Prior to initiating AMJEVITA and periodically during therapy, evaluate patients for active tuberculosis and test for latent infection [see Warnings and Precautions (5.1)].

2.8 General Considerations for Administration

AMJEVITA is intended for use under the guidance and supervision of a physician. A patient may self-inject AMJEVITA or a caregiver may inject AMJEVITA using either the AMJEVITA prefilled SureClick autoinjector or prefilled syringe if a physician determines that it is appropriate, and with medical follow-up, as necessary, after proper training in subcutaneous injection technique.

AMJEVITA can be taken out of the refrigerator for 15 to 30 minutes before injecting to allow the liquid to come to room temperature. Do not remove the cap or cover while allowing it to reach room temperature. Carefully inspect the solution in the AMJEVITA prefilled SureClick autoinjector or prefilled syringe for particulate matter and discoloration prior to subcutaneous administration. If particulates and discolorations are noted, do not use the product. AMJEVITA does not contain preservatives; therefore, discard unused portions of drug remaining from the syringe.

Instruct patients using the AMJEVITA prefilled SureClick autoinjector or prefilled syringe to inject the full amount in the syringe, according to the directions provided in the Instructions for Use [see Instructions for Use].

Injections should occur at separate sites in the thigh or abdomen. Rotate injection sites and do not give injections into areas where the skin is tender, bruised, red or hard.

If a dose is missed, administer the dose as soon as possible. Thereafter, resume dosing at the regular scheduled time.

3 DOSAGE FORMS AND STRENGTHS

AMJEVITA is a clear, colorless to slightly yellow solution available as:

- Prefilled SureClick Autoinjector
  - Injection: 80mg/0.8 mL in a single-dose prefilled SureClick autoinjector.
  - Injection: 40mg/0.4 mL in a single-dose prefilled SureClick autoinjector.
- Prefilled Syringe
  - Injection: 80 mg/0.8 mL in a single-dose prefilled glass syringe.
  - Injection: 40 mg/0.4 mL in a single-dose prefilled glass syringe.
  - Injection: 20 mg/0.2 mL in a single-dose prefilled glass syringe.

4 CONTRAINDICATIONS

None.

5 WARNINGS AND PRECAUTIONS

5.1 Serious Infections

Patients treated with adalimumab products including AMJEVITA are at increased risk for developing serious infections involving various organ systems and sites that may lead to hospitalization or death. Opportunistic infections due to bacterial, mycobacterial, invasive fungal, viral, parasitic, or other opportunistic pathogens including aspergillosis, blastomycosis, candidiasis, coccidioidomycosis, histoplasmosis, legionellosis, listeriosis, pneumocystosis and tuberculosis have been reported with TNF-blockers. Patients have frequently presented with disseminated rather than localized disease.

The concomitant use of a TNF-blocker and abatacept or anakinra was associated with a higher risk of serious infections in patients with rheumatoid arthritis (RA); therefore, the concomitant use of AMJEVITA and these biologic products is not recommended in the treatment of patients with RA [see Warnings and Precautions (5.7, 5.11)and Drug Interactions (7.2)] .

Treatment with AMJEVITA should not be initiated in patients with an active infection, including localized infections. Patients 65 years of age and older, patients with co-morbid conditions and/or patients taking concomitant immunosuppressants (such as corticosteroids or methotrexate), may be at greater risk of infection. Consider the risks and benefits of treatment prior to initiating therapy in patients:

- with chronic or recurrent infection;
- who have been exposed to tuberculosis;
- with a history of an opportunistic infection;
- who have resided or traveled in areas of endemic tuberculosis or endemic mycoses, such as histoplasmosis, coccidioidomycosis, or blastomycosis; or
- with underlying conditions that may predispose them to infection.

Tuberculosis

Cases of reactivation of tuberculosis and new onset tuberculosis infections have been reported in patients receiving adalimumab products, including patients who have previously received treatment for latent or active tuberculosis. Reports included cases of pulmonary and extrapulmonary (i.e., disseminated) tuberculosis. Evaluate patients for tuberculosis risk factors and test for latent infection prior to initiating AMJEVITA and periodically during therapy.

Treatment of latent tuberculosis infection prior to therapy with TNF blocking agents has been shown to reduce the risk of tuberculosis reactivation during therapy. Prior to initiating AMJEVITA, assess if treatment for latent tuberculosis is needed; and consider an induration of ≥ 5 mm a positive tuberculin skin test result, even for patients previously vaccinated with Bacille Calmette-Guerin (BCG).

Consider anti-tuberculosis therapy prior to initiation of AMJEVITA in patients with a past history of latent or active tuberculosis in whom an adequate course of treatment cannot be confirmed, and for patients with a negative test for latent tuberculosis but having risk factors for tuberculosis infection. Despite prophylactic treatment for tuberculosis, cases of reactivated tuberculosis have occurred in patients treated with adalimumab products. Consultation with a physician with expertise in the treatment of tuberculosis is recommended to aid in the decision whether initiating anti-tuberculosis therapy is appropriate for an individual patient.

Strongly consider tuberculosis in the differential diagnosis in patients who develop a new infection during AMJEVITA treatment, especially in patients who have previously or recently traveled to countries with a high prevalence of tuberculosis, or who have had close contact with a person with active tuberculosis.

Monitoring

Closely monitor patients for the development of signs and symptoms of infection during and after treatment with AMJEVITA, including the development of tuberculosis in patients who tested negative for latent tuberculosis infection prior to initiating therapy. Tests for latent tuberculosis infection may also be falsely negative while on therapy with AMJEVITA.

Discontinue AMJEVITA if a patient develops a serious infection or sepsis. For a patient who develops a new infection during treatment with AMJEVITA, closely monitor them, perform a prompt and complete diagnostic workup appropriate for an immunocompromised patient, and initiate appropriate antimicrobial therapy.

Invasive Fungal Infections

If patients develop a serious systemic illness and they reside or travel in regions where mycoses are endemic, consider invasive fungal infection in the differential diagnosis. Antigen and antibody testing for histoplasmosis may be negative in some patients with active infection.

Consider appropriate empiric antifungal therapy, taking into account both the risk for severe fungal infection and the risks of antifungal therapy, while a diagnostic workup is being performed. To aid in the management of such patients, consider consultation with a physician with expertise in the diagnosis and treatment of invasive fungal infections.

5.2 Malignancies

Consider the risks and benefits of TNF-blocker treatment including AMJEVITA prior to initiating therapy in patients with a known malignancy other than a successfully treated non-melanoma skin cancer (NMSC) or when considering continuing a TNF-blocker in patients who develop a malignancy.

Malignancies in Adults

In the controlled portions of clinical trials of some TNF-blockers, including adalimumab products, more cases of malignancies have been observed among TNF-blocker-treated adult patients compared to control-treated adult patients. During the controlled portions of 39 global adalimumab clinical trials in adult patients with rheumatoid arthritis (RA), psoriatic arthritis (PsA), ankylosing spondylitis (AS), Crohn's disease (CD), ulcerative colitis (UC), plaque psoriasis (Ps), hidradenitis suppurativa (HS) and uveitis (UV), malignancies, other than non-melanoma (basal cell and squamous cell) skin cancer, were observed at a rate (95% confidence interval) of 0.7 (0.48, 1.03) per 100 patient-years among 7973 adalimumab-treated patients versus a rate of 0.7 (0.41, 1.17) per 100 patient-years among 4848 control-treated patients (median duration of treatment of 4 months for adalimumab-treated patients and 4 months for control-treated patients). In 52 global controlled and uncontrolled clinical trials of adalimumab in adult patients with RA, PsA, AS, CD, UC, Ps, HS and UV, the most frequently observed malignancies, other than lymphoma and NMSC, were breast, colon, prostate, lung, and melanoma. The malignancies in adalimumab-treated patients in the controlled and uncontrolled portions of the studies were similar in type and number to what would be expected in the general U.S. population according to the SEER database (adjusted for age, gender, and race).^1

In controlled trials of other TNF-blockers in adult patients at higher risk for malignancies (i.e., patients with COPD with a significant smoking history and cyclophosphamide-treated patients with Wegener's granulomatosis), a greater portion of malignancies occurred in the TNF-blocker group compared to the control group.

Non-Melanoma Skin Cancer

During the controlled portions of 39 global adalimumab clinical trials in adult patients with RA, PsA, AS, CD, UC, Ps, HS and UV, the rate (95% confidence interval) of NMSC was 0.8 (0.52, 1.09) per 100 patient-years among adalimumab-treated patients and 0.2 (0.10, 0.59) per 100 patient-years among control-treated patients. Examine all patients, and in particular patients with a medical history of prior prolonged immunosuppressant therapy or psoriasis patients with a history of PUVA treatment for the presence of NMSC prior to and during treatment with AMJEVITA.

Lymphoma and Leukemia

In the controlled portions of clinical trials of all the TNF-blockers in adults, more cases of lymphoma have been observed among TNF-blocker-treated patients compared to control-treated patients. In the controlled portions of 39 global adalimumab clinical trials in adult patients with RA, PsA, AS, CD, UC, Ps, HS and UV, 2 lymphomas occurred among 7973 adalimumab treated patients versus 1 among 4848 control-treated patients. In 52 global controlled and uncontrolled clinical trials of adalimumab in adult patients with RA, PsA, AS, CD, UC, Ps, HS and UV, with a median duration of approximately 0.7 years, including 24,605 patients and over 40,215 patient-years of adalimumab, the observed rate of lymphomas was approximately 0.11 per 100 patient-years. This is approximately 3-fold higher than expected in the general U.S. population according to the SEER database (adjusted for age, gender, and race).^1Rates of lymphoma in clinical trials of adalimumab cannot be compared to rates of lymphoma in clinical trials of other TNF-blockers and may not predict the rates observed in a broader patient population. Patients with RA and other chronic inflammatory diseases, particularly those with highly active disease and/or chronic exposure to immunosuppressant therapies, may be at a higher risk (up to several fold) than the general population for the development of lymphoma, even in the absence of TNF-blockers. Post-marketing cases of acute and chronic leukemia have been reported in association with TNF-blocker use in RA and other indications. Even in the absence of TNF-blocker therapy, patients with RA may be at a higher risk (approximately 2-fold) than the general population for the development of leukemia.

Malignancies in Pediatric Patients and Young Adults

Malignancies, some fatal, have been reported among children, adolescents, and young adults who received treatment with TNF-blockers (initiation of therapy ≤ 18 years of age), of which AMJEVITA is a member. Approximately half the cases were lymphomas, including Hodgkin's and non-Hodgkin's lymphoma. The other cases represented a variety of different malignancies and included rare malignancies usually associated with immunosuppression and malignancies that are not usually observed in children and adolescents. The malignancies occurred after a median of 30 months of therapy (range 1 to 84 months). Most of the patients were receiving concomitant immunosuppressants. These cases were reported post marketing and are derived from a variety of sources including registries and spontaneous post-marketing reports.

Post-marketing cases of hepatosplenic T-cell lymphoma (HSTCL), a rare type of T-cell lymphoma, have been reported in patients treated with TNF-blockers including adalimumab products. These cases have had a very aggressive disease course and have been fatal. The majority of reported TNF-blocker cases have occurred in patients with Crohn's disease or ulcerative colitis and the majority were in adolescent and young adult males. Almost all of these patients had received treatment with the immunosuppressants azathioprine or 6-mercaptopurine (6–MP) concomitantly with a TNF-blocker at or prior to diagnosis. It is uncertain whether the occurrence of HSTCL is related to use of a TNF-blocker or a TNF-blocker in combination with these other immunosuppressants. The potential risk with the combination of azathioprine or 6-mercaptopurine and AMJEVITA should be carefully considered.

5.3 Hypersensitivity Reactions

Anaphylaxis and angioneurotic edema have been reported following administration of adalimumab products. If an anaphylactic or other serious allergic reaction occurs, immediately discontinue administration of AMJEVITA and institute appropriate therapy. In clinical trials of adalimumab, hypersensitivity reactions (e.g., rash, anaphylactoid reaction, fixed drug reaction, non-specified drug reaction, urticaria) have been observed.

5.4 Hepatitis B Virus Reactivation

Use of TNF-blockers, including AMJEVITA, may increase the risk of reactivation of hepatitis B virus (HBV) in patients who are chronic carriers of this virus. In some instances, HBV reactivation occurring in conjunction with TNF-blocker therapy has been fatal. The majority of these reports have occurred in patients concomitantly receiving other medications that suppress the immune system, which may also contribute to HBV reactivation. Evaluate patients at risk for HBV infection for prior evidence of HBV infection before initiating TNF-blocker therapy. Exercise caution in prescribing TNF-blockers for patients identified as carriers of HBV. Adequate data are not available on the safety or efficacy of treating patients who are carriers of HBV with anti-viral therapy in conjunction with TNF-blocker therapy to prevent HBV reactivation. For patients who are carriers of HBV and require treatment with TNF-blockers, closely monitor such patients for clinical and laboratory signs of active HBV infection throughout therapy and for several months following termination of therapy. In patients who develop HBV reactivation, stop AMJEVITA and initiate effective anti-viral therapy with appropriate supportive treatment. The safety of resuming TNF-blocker therapy after HBV reactivation is controlled is not known. Therefore, exercise caution when considering resumption of AMJEVITA therapy in this situation and monitor patients closely.

5.5 Neurologic Reactions

Use of TNF blocking agents, including adalimumab products, has been associated with rare cases of new onset or exacerbation of clinical symptoms and/or radiographic evidence of central nervous system demyelinating disease, including multiple sclerosis (MS) and optic neuritis, and peripheral demyelinating disease, including Guillain-Barré syndrome. Exercise caution in considering the use of AMJEVITA in patients with preexisting or recent-onset central or peripheral nervous system demyelinating disorders; discontinuation of AMJEVITA should be considered if any of these disorders develop. There is a known association between intermediate uveitis and central demyelinating disorders.

5.6 Hematological Reactions

Rare reports of pancytopenia including aplastic anemia have been reported with TNF blocking agents. Adverse reactions of the hematologic system, including medically significant cytopenia (e.g., thrombocytopenia, leukopenia) have been infrequently reported with adalimumab products. The causal relationship of these reports to adalimumab products remains unclear. Advise all patients to seek immediate medical attention if they develop signs and symptoms suggestive of blood dyscrasias or infection (e.g., persistent fever, bruising, bleeding, pallor) while on AMJEVITA. Consider discontinuation of AMJEVITA therapy in patients with confirmed significant hematologic abnormalities.

5.7 Increased Risk of Infection When Used with Anakinra

Concurrent use of anakinra (an interleukin-1 antagonist) and another TNF-blocker, was associated with a greater proportion of serious infections and neutropenia and no added benefit compared with the TNF-blocker alone in patients with RA. Therefore, the combination of AMJEVITA and anakinra is not recommended [see Drug Interactions (7.2)].

5.8 Heart Failure

Cases of worsening congestive heart failure (CHF) and new onset CHF have been reported with TNF-blockers. Cases of worsening CHF have also been observed with adalimumab products. Adalimumab products have not been formally studied in patients with CHF; however, in clinical trials of another TNF-blocker, a higher rate of serious CHF-related adverse reactions was observed. Exercise caution when using AMJEVITA in patients who have heart failure and monitor them carefully.

5.9 Autoimmunity

Treatment with adalimumab products may result in the formation of autoantibodies and, rarely, in the development of a lupus-like syndrome. If a patient develops symptoms suggestive of a lupus-like syndrome following treatment with AMJEVITA, discontinue treatment [see Adverse Reactions (6.1)].

5.10 Immunizations

In a placebo-controlled clinical trial of patients with RA, no difference was detected in anti-pneumococcal antibody response between adalimumab and placebo treatment groups when the pneumococcal polysaccharide vaccine and influenza vaccine were administered concurrently with adalimumab. Similar proportions of patients developed protective levels of anti-influenza antibodies between adalimumab and placebo treatment groups; however, titers in aggregate to influenza antigens were moderately lower in patients receiving adalimumab. The clinical significance of this is unknown. Patients on AMJEVITA may receive concurrent vaccinations, except for live vaccines. No data are available on the secondary transmission of infection by live vaccines in patients receiving adalimumab products.

It is recommended that pediatric patients, if possible, be brought up to date with all immunizations in agreement with current immunization guidelines prior to initiating AMJEVITA therapy. Patients on AMJEVITA may receive concurrent vaccinations, except for live vaccines.

The safety of administering live or live-attenuated vaccines in infants exposed to adalimumab products in uterois unknown. Risks and benefits should be considered prior to vaccinating (live or live-attenuated) exposed infants [see Use in Specific Populations (8.1, 8.4)].

5.11 Increased Risk of Infection When Used with Abatacept

In controlled trials, the concurrent administration of TNF-blockers and abatacept was associated with a greater proportion of serious infections than the use of a TNF-blocker alone; the combination therapy, compared to the use of a TNF-blocker alone, has not demonstrated improved clinical benefit in the treatment of RA. Therefore, the combination of abatacept with TNF-blockers including AMJEVITA is not recommended [see Drug Interactions (7.2)] .

6 ADVERSE REACTIONS

The following clinically significant adverse reactions are described elsewhere in the labeling:

- Serious Infections [see Warnings and Precautions (5.1)]
- Malignancies [see Warnings and Precautions (5.2)]
- Hypersensitivity Reactions [see Warnings and Precautions (5.3)]
- Hepatitis B Virus Reactivation [see Warnings and Precautions (5.4)]
- Neurologic Reactions [see Warnings and Precautions (5.5)]
- Hematological Reactions [see Warnings and Precautions (5.6)]
- Heart Failure [see Warnings and Precautions (5.8)]
- Autoimmunity [see Warnings and Precautions (5.9)]

6.1 Clinical Trials Experience

Because clinical trials are conducted under widely varying conditions, adverse reaction rates observed in the clinical trials of a drug cannot be directly compared to rates in the clinical trials of another drug and may not reflect the rates observed in practice.

The most common adverse reaction with adalimumab was injection site reactions. In placebo-controlled trials, 20% of patients treated with adalimumab developed injection site reactions (erythema and/or itching, hemorrhage, pain or swelling), compared to 14% of patients receiving placebo. Most injection site reactions were described as mild and generally did not necessitate drug discontinuation.

The proportion of patients who discontinued treatment due to adverse reactions during the double-blind, placebo-controlled portion of studies in patients with RA (i.e., Studies RA-I, RA-II, RA-III and RA-IV) was 7% for patients taking adalimumab and 4% for placebo-treated patients. The most common adverse reactions leading to discontinuation of adalimumab in these RA studies were clinical flare reaction (0.7%), rash (0.3%) and pneumonia (0.3%).

Infections

In the controlled portions of 39 global adalimumab clinical trials in adult patients with RA, PsA, AS, CD, UC, Ps, HS and UV, the rate of serious infections was 4.3 per 100 patient-years in 7973 adalimumab-treated patients versus a rate of 2.9 per 100 patient-years in 4848 control-treated patients. Serious infections observed included pneumonia, septic arthritis, prosthetic and post-surgical infections, erysipelas, cellulitis, diverticulitis, and pyelonephritis [see Warnings and Precautions (5.1)].

Tuberculosis and Opportunistic Infections

In 52 global controlled and uncontrolled clinical trials in RA, PsA, AS, CD, UC, Ps, HS and UV that included 24,605 adalimumab-treated patients, the rate of reported active tuberculosis was 0.20 per 100 patient-years and the rate of positive PPD conversion was 0.09 per 100 patient-years. In a subgroup of 10,113 U.S. and Canadian adalimumab-treated patients, the rate of reported active TB was 0.05 per 100 patient-years and the rate of positive PPD conversion was 0.07 per 100 patient-years. These trials included reports of miliary, lymphatic, peritoneal, and pulmonary TB. Most of the TB cases occurred within the first eight months after initiation of therapy and may reflect recrudescence of latent disease. In these global clinical trials, cases of serious opportunistic infections have been reported at an overall rate of 0.05 per 100 patient-years. Some cases of serious opportunistic infections and TB have been fatal [see Warnings and Precautions (5.1)].

Autoantibodies

In the rheumatoid arthritis controlled trials, 12% of patients treated with adalimumab and 7% of placebo-treated patients that had negative baseline ANA titers developed positive titers at week 24. Two patients out of 3046 treated with adalimumab developed clinical signs suggestive of new-onset lupus-like syndrome. The patients improved following discontinuation of therapy. No patients developed lupus nephritis or central nervous system symptoms. The impact of long-term treatment with adalimumab products on the development of autoimmune diseases is unknown.

Liver Enzyme Elevations

There have been reports of severe hepatic reactions including acute liver failure in patients receiving TNF-blockers. In controlled Phase 3 trials of adalimumab (40 mg SC every other week) in patients with RA, PsA, and AS with control period duration ranging from 4 to 104 weeks, ALT elevations ≥ 3 × ULN occurred in 3.5% of adalimumab-treated patients and 1.5% of control-treated patients. Since many of these patients in these trials were also taking medications that cause liver enzyme elevations (e.g., NSAIDs, MTX), the relationship between adalimumab and the liver enzyme elevations is not clear. In a controlled Phase 3 trial of adalimumab in patients with polyarticular JIA who were 4 to 17 years, ALT elevations ≥ 3 × ULN occurred in 4.4% of adalimumab-treated patients and 1.5% of control-treated patients (ALT more common than AST); liver enzyme test elevations were more frequent among those treated with the combination of adalimumab and MTX than those treated with adalimumab alone. In general, these elevations did not lead to discontinuation of adalimumab treatment. No ALT elevations ≥ 3 × ULN occurred in the open-label study of adalimumab in patients with polyarticular JIA who were 2 to < 4 years.

In controlled Phase 3 trials of adalimumab (initial doses of 160 mg and 80 mg, or 80 mg and 40 mg on Days 1 and 15, respectively, followed by 40 mg every other week) in adult patients with CD with a control period duration ranging from 4 to 52 weeks, ALT elevations ≥ 3 × ULN occurred in 0.9% of adalimumab-treated patients and 0.9% of control-treated patients. In the Phase 3 trial of adalimumab in pediatric patients with Crohn's disease which evaluated efficacy and safety of two body weight based maintenance dose regimens following body weight based induction therapy up to 52 weeks of treatment, ALT elevations ≥ 3 × ULN occurred in 2.6% (5/192) of patients, of whom 4 were receiving concomitant immunosuppressants at baseline; none of these patients discontinued due to abnormalities in ALT tests. In controlled Phase 3 trials of adalimumab (initial doses of 160 mg and 80 mg on Days 1 and 15, respectively, followed by 40 mg every other week) in adult patients with UC with control period duration ranging from 1 to 52 weeks, ALT elevations ≥ 3 × ULN occurred in 1.5% of adalimumab-treated patients and 1.0% of control-treated patients. In controlled Phase 3 trials of adalimumab (initial dose of 80 mg then 40 mg every other week) in patients with Ps with control period duration ranging from 12 to 24 weeks, ALT elevations ≥ 3 × ULN occurred in 1.8% of adalimumab-treated patients and 1.8% of control-treated patients. In controlled trials of adalimumab (initial doses of 160 mg at Week 0 and 80 mg at Week 2, followed by 40 mg every week starting at Week 4), in subjects with HS with a control period duration ranging from 12 to 16 weeks, ALT elevations ≥ 3 × ULN occurred in 0.3% of adalimumab-treated subjects and 0.6% of control-treated subjects. In controlled trials of adalimumab (initial doses of 80 mg at Week 0, followed by 40 mg every other week starting at Week 1) in adult patients with uveitis with an exposure of 165.4 PYs and 119.8 PYs in adalimumab-treated and control-treated patients, respectively, ALT elevations ≥ 3 × ULN occurred in 2.4% of adalimumab-treated patients and 2.4% of control-treated patients.

Other Adverse Reactions

Rheumatoid Arthritis Clinical Studies

The data described below reflect exposure to adalimumab in 2468 patients, including 2073 exposed for 6 months, 1497 exposed for greater than one year and 1380 in adequate and well-controlled studies (Studies RA-I, RA-II, RA-III, and RA-IV). Adalimumab was studied primarily in placebo-controlled trials and in long-term follow up studies for up to 36 months duration. The population had a mean age of 54 years, 77% were female, 91% were Caucasian and had moderately to severely active rheumatoid arthritis. Most patients received 40 mg adalimumab every other week [see Clinical Studies (14.1)] .

Table 1 summarizes reactions reported at a rate of at least 5% in patients treated with adalimumab 40 mg every other week compared to placebo and with an incidence higher than placebo. In Study RA-III, the types and frequencies of adverse reactions in the second year open-label extension were similar to those observed in the one-year double-blind portion.

Table 1. Adverse Reactions Reported by ≥ 5% of Patients Treated with Adalimumab During Placebo-Controlled Period of Pooled RA Studies (Studies RA-I, RA-II, RA-III, and RA-IV)
 | Adalimumab 40 mg subcutaneous Every Other Week | Placebo
 | (N = 705) | (N = 690)
Adverse Reaction (Preferred Term)
Respiratory
Upper respiratory infection | 17% | 13%
Sinusitis | 11% | 9%
Flu syndrome | 7% | 6%
Gastrointestinal
Nausea | 9% | 8%
Abdominal pain | 7% | 4%
Laboratory Tests [Laboratory test abnormalities were reported as adverse reactions in European trials]
Laboratory test abnormal | 8% | 7%
Hypercholesterolemia | 6% | 4%
Hyperlipidemia | 7% | 5%
Hematuria | 5% | 4%
Alkaline phosphatase increased | 5% | 3%
Other
Headache | 12% | 8%
Rash | 12% | 6%
Accidental injury | 10% | 8%
Injection site reaction [Does not include injection site erythema, itching, hemorrhage, pain or swelling] | 8% | 1%
Back pain | 6% | 4%
Urinary tract infection | 8% | 5%
Hypertension | 5% | 3%

Less Common Adverse Reactions in Rheumatoid Arthritis Clinical Studies

Other infrequent serious adverse reactions that do not appear in the Warnings and Precautions or Adverse Reaction sections that occurred at an incidence of less than 5% in adalimumab-treated patients in RA studies were:

Body As A Whole:Pain in extremity, pelvic pain, surgery, thorax pain

Cardiovascular System:Arrhythmia, atrial fibrillation, chest pain, coronary artery disorder, heart arrest, hypertensive encephalopathy, myocardial infarct, palpitation, pericardial effusion, pericarditis, syncope, tachycardia

Digestive System:Cholecystitis, cholelithiasis, esophagitis, gastroenteritis, gastrointestinal hemorrhage, hepatic necrosis, vomiting

Endocrine System:Parathyroid disorder

Hemic And Lymphatic System:Agranulocytosis, polycythemia

Metabolic And Nutritional Disorders:Dehydration, healing abnormal, ketosis, paraproteinemia, peripheral edema

Musculo-Skeletal System:Arthritis, bone disorder, bone fracture (not spontaneous), bone necrosis, joint disorder, muscle cramps, myasthenia, pyogenic arthritis, synovitis, tendon disorder

Neoplasia:Adenoma

Nervous System:Confusion, paresthesia, subdural hematoma, tremor

Respiratory System:Asthma, bronchospasm, dyspnea, lung function decreased, pleural effusion

Special Senses:Cataract

Thrombosis:Thrombosis leg

Urogenital System:Cystitis, kidney calculus, menstrual disorder

Juvenile Idiopathic Arthritis Clinical Studies

In general, the adverse reactions in the adalimumab-treated patients in the polyarticular juvenile idiopathic arthritis (JIA) trials (Studies JIA-I and JIA-II) [see Clinical Studies (14.2)] were similar in frequency and type to those seen in adult patients [see Warnings and Precautions (5), Adverse Reactions (6)] . Important findings and differences from adults are discussed in the following paragraphs.

In Study JIA-I, adalimumab was studied in 171 patients who were 4 to 17 years of age, with polyarticular JIA. Severe adverse reactions reported in the study included neutropenia, streptococcal pharyngitis, increased aminotransferases, herpes zoster, myositis, metrorrhagia, and appendicitis. Serious infections were observed in 4% of patients within approximately 2 years of initiation of treatment with adalimumab and included cases of herpes simplex, pneumonia, urinary tract infection, pharyngitis, and herpes zoster.

In Study JIA-I, 45% of patients experienced an infection while receiving adalimumab with or without concomitant MTX in the first 16 weeks of treatment. The types of infections reported in adalimumab-treated patients were generally similar to those commonly seen in polyarticular JIA patients who are not treated with TNF-blockers. Upon initiation of treatment, the most common adverse reactions occurring in this patient population treated with adalimumab were injection site pain and injection site reaction (19% and 16%, respectively). A less commonly reported adverse event in patients receiving adalimumab was granuloma annulare which did not lead to discontinuation of adalimumab treatment.

In the first 48 weeks of treatment in Study JIA-I, non-serious hypersensitivity reactions were seen in approximately 6% of patients and included primarily localized allergic hypersensitivity reactions and allergic rash.

In Study JIA-I, 10% of patients treated with adalimumab who had negative baseline anti-dsDNA antibodies developed positive titers after 48 weeks of treatment. No patient developed clinical signs of autoimmunity during the clinical trial.

Approximately 15% of patients treated with adalimumab developed mild-to-moderate elevations of creatine phosphokinase (CPK) in Study JIA-I. Elevations exceeding 5 times the upper limit of normal were observed in several patients. CPK concentrations decreased or returned to normal in all patients. Most patients were able to continue adalimumab without interruption.

In Study JIA-II, adalimumab was studied in 32 patients who were 2 to < 4 years of age or 4 years of age and older weighing < 15 kg with polyarticular JIA. The safety profile for this patient population was similar to the safety profile seen in patients 4 to 17 years of age with polyarticular JIA.

In Study JIA-II, 78% of patients experienced an infection while receiving adalimumab. These included nasopharyngitis, bronchitis, upper respiratory tract infection, otitis media, and were mostly mild to moderate in severity. Serious infections were observed in 9% of patients receiving adalimumab in the study and included dental caries, rotavirus gastroenteritis, and varicella.

In Study JIA-II, non-serious allergic reactions were observed in 6% of patients and included intermittent urticaria and rash, which were all mild in severity.

Psoriatic Arthritis and Ankylosing Spondylitis Clinical Studies

Adalimumab has been studied in 395 patients with psoriatic arthritis (PsA) in two placebo-controlled trials and in an open-label study and in 393 patients with ankylosing spondylitis (AS) in two placebo-controlled studies [see Clinical Studies (14.3, 14.4)] . The safety profile for patients with PsA and AS treated with adalimumab 40 mg every other week was similar to the safety profile seen in patients with RA, adalimumab Studies RA-I through IV.

Crohn's Disease Clinical Studies

Adults:The safety profile of adalimumab in 1478 adult patients with Crohn's disease (CD) from four placebo-controlled and two open-label extension studies [see Clinical Studies (14.5)] was similar to the safety profile seen in patients with RA.

Pediatric Patients 6 Years to 17 Years:The safety profile of adalimumab in 192 pediatric patients from one double-blind study (Study PCD-I) and one open-label extension study [see Clinical Studies (14.6)] was similar to the safety profile seen in adult patients with CD.

During the 4-week open-label induction phase of Study PCD-I, the most common adverse reactions occurring in the pediatric population treated with adalimumab were injection site pain and injection site reaction (6% and 5%, respectively).

A total of 67% of children experienced an infection while receiving adalimumab in Study PCD-I. These included upper respiratory tract infection and nasopharyngitis.

A total of 5% of children experienced a serious infection while receiving adalimumab in Study PCD-I. These included viral infection, device related sepsis (catheter), gastroenteritis, H1N1 influenza, and disseminated histoplasmosis.

In Study PCD-I, allergic reactions were observed in 5% of children which were all non-serious and were primarily localized reactions.

Ulcerative Colitis Clinical Studies

Adults:The safety profile of adalimumab in 1010 adult patients with ulcerative colitis (UC) from two placebo-controlled studies and one open-label extension study [see Clinical Studies (14.7)] was similar to the safety profile seen in patients with RA.

Plaque Psoriasis Clinical Studies

Adalimumab has been studied in 1696 subjects with plaque psoriasis (Ps) in placebo controlled and open-label extension studies [see Clinical Studies (14.8)] . The safety profile for subjects with Ps treated with adalimumab was similar to the safety profile seen in subjects with RA with the following exceptions. In the placebo-controlled portions of the clinical trials in Ps subjects, adalimumab-treated subjects had a higher incidence of arthralgia when compared to controls (3% vs.1%).

Hidradenitis Suppurativa Clinical Studies

Adalimumab has been studied in 727 subjects with hidradenitis suppurativa (HS) in three placebo-controlled studies and one open-label extension study [see Clinical Studies (14.9)] . The safety profile for subjects with HS treated with adalimumab weekly was consistent with the known safety profile of adalimumab.

Flare of HS, defined as ≥25% increase from baseline in abscesses and inflammatory nodule counts and with a minimum of 2 additional lesions, was documented in 22 (22%) of the 100 subjects who were withdrawn from adalimumab treatment following the primary efficacy timepoint in two studies.

Uveitis Clinical Studies

Adalimumab has been studied in 464 adult patients with uveitis (UV) in placebo-controlled and open-label extension studies [see Clinical Studies (14.10)] . The safety profile for patients with UV treated with adalimumab was similar to the safety profile seen in patients with RA.

6.2 Immunogenicity

As with all therapeutic proteins, there is potential for immunogenicity. The detection of antibody formation is highly dependent on the sensitivity and specificity of the assay. Additionally, the observed incidence of antibody (including neutralizing antibody) positivity in an assay may be influenced by several factors including assay methodology, sample handling, timing of sample collection, concomitant medications, and underlying disease. For these reasons, comparison of the incidence of antibodies in the studies described below with the incidence of antibodies in other studies or to other adalimumab products may be misleading.

There are two assays that have been used to measure anti-adalimumab antibodies. With the ELISA, antibodies to adalimumab could be detected only when serum adalimumab concentrations were < 2 mcg/mL. The ECL assay can detect anti-adalimumab antibody titers independent of adalimumab concentrations in the serum samples. The incidence of anti-adalimumab antibody (AAA) development in patients treated with adalimumab are presented in Table 2.

Table 2. Anti-Adalimumab Antibody Development Determined by ELISA and ECL Assay in Patients Treated with Adalimumab
Indications |  | Study Duration | Anti-Adalimumab Antibody Incidence by ELISA (n/N) |  | Anti-Adalimumab Antibody Incidence by ECL Assay (n/N)
 |  |  | In all patients who received adalimumab | In patients with serum adalimumab concentrations < 2 mcg/mL
Rheumatoid Arthritis [In patients receiving concomitant methotrexate (MTX), the incidence of anti-adalimumab antibody was 1% compared to 12% with adalimumab monotherapy] |  | 6 to 12 months | 5% (58/1062) | NR | NA
Juvenile Idiopathic Arthritis (JIA) | 4 to 17 years of age [In patients receiving concomitant MTX, the incidence of anti-adalimumab antibody was 6% compared to 26% with adalimumab monotherapy] | 48 weeks | 16% (27/171) | NR | NA
Juvenile Idiopathic Arthritis (JIA) | 2 to 4 years of age or ≥ 4 years of age and weighing < 15 kg | 24 weeks | 7% (1/15) [This patient received concomitant MTX] | NR | NA
Psoriatic Arthritis [In patients receiving concomitant MTX, the incidence of antibody development was 7% compared to 1% in RA] |  | 48 weeks [Subjects enrolled after completing 2 previous studies of 24 weeks or 12 weeks of treatments] | 13% (24/178) | NR | NA
Ankylosing Spondylitis |  | 24 weeks | 9% (16/185) | NR | NA
Adult Crohn's Disease |  | 56 weeks | 3% (7/269) | 8% (7/86) | NA
Pediatric Crohn's Disease |  | 52 weeks | 3% (6/182) | 10% (6/58) | NA
Adult Ulcerative Colitis |  | 52 weeks | 5% (19/360) | 21% (19/92) | NA
Plaque Psoriasis [In plaque psoriasis patients who were on adalimumab monotherapy and subsequently withdrawn from the treatment, the rate of antibodies to adalimumab after retreatment was similar to the rate observed prior to withdrawal] |  | Up to 52 weeks [One 12-week Phase 2 study and one 52-week Phase 3 study] | 8% (77/920) | 21% (77/372) | NA
Hidradenitis Suppurativa |  | 36 weeks | 7% (30/461) | 28% (58/207) [Among subjects in the two Phase 3 studies who stopped adalimumab treatment for up to 24 weeks and in whom adalimumab serum levels subsequently declined to < 2 mcg/mL (approximately 22% of total subjects studied)] | 61% (272/445 [No apparent association between antibody development and safety was observed]
Non-infectious Uveitis |  | 52 weeks | 5% (12/249) | 21% (12/57) | 40% (99/249) [No correlation of antibody development to safety or efficacy outcomes was observed]
n: number of patients with anti-adalimumab antibody; NR: not reported; NA: Not applicable (not performed)

Rheumatoid Arthritis and Psoriatic Arthritis:Patients in Studies RA-I, RA-II, and RA-III were tested at multiple time points for antibodies to adalimumab using the ELISA during the 6- to 12-month period. No apparent correlation of antibody development to adverse reactions was observed. With monotherapy, patients receiving every other week dosing may develop antibodies more frequently than those receiving weekly dosing. In patients receiving the recommended dosage of 40 mg every other week as monotherapy, the ACR 20 response was lower among antibody-positive patients than among antibody-negative patients. The long-term immunogenicity of adalimumab products is unknown.

6.3 Postmarketing Experience

The following adverse reactions have been identified during post-approval use of adalimumab products. Because these reactions are reported voluntarily from a population of uncertain size, it is not always possible to reliably estimate their frequency or establish a causal relationship to adalimumab products exposure.

Gastrointestinal disorders:Diverticulitis, large bowel perforations including perforations associated with diverticulitis and appendiceal perforations associated with appendicitis, pancreatitis

General disorders and administration site conditions:Pyrexia

Hepato-biliary disorders:Liver failure, hepatitis

Immune system disorders:Sarcoidosis

Neoplasms benign, malignant and unspecified (including cysts and polyps):Merkel Cell Carcinoma (neuroendocrine carcinoma of the skin)

Nervous system disorders:Demyelinating disorders (e.g., optic neuritis, Guillain-Barré syndrome), cerebrovascular accident

Respiratory disorders:Interstitial lung disease, including pulmonary fibrosis, pulmonary embolism

Skin reactions:Stevens Johnson Syndrome, cutaneous vasculitis, erythema multiforme, new or worsening psoriasis (all sub types including pustular and palmoplantar), alopecia, lichenoid skin reaction

Vascular disorders:Systemic vasculitis, deep vein thrombosis

7 DRUG INTERACTIONS

7.1 Methotrexate

Adalimumab has been studied in rheumatoid arthritis (RA) patients taking concomitant methotrexate (MTX). Although MTX reduced the apparent adalimumab clearance, the data do not suggest the need for dose adjustment of either AMJEVITA or MTX [see Clinical Pharmacology (12.3)] .

7.2 Biological Products

In clinical studies in patients with RA, an increased risk of serious infections has been observed with the combination of TNF‑blockers with anakinra or abatacept, with no added benefit; therefore, use of AMJEVITA with abatacept or anakinra is not recommended in patients with RA [see Warnings and Precautions (5.7, 5.11)] . A higher rate of serious infections has also been observed in patients with RA treated with rituximab who received subsequent treatment with a TNF-blocker. There is insufficient information regarding the concomitant use of AMJEVITA and other biologic products for the treatment of RA, PsA, AS, CD, UC, Ps, HS and UV. Concomitant administration of AMJEVITA with other biologic DMARDs (e.g., anakinra and abatacept) or other TNF‑blockers is not recommended based upon the possible increased risk for infections and other potential pharmacological interactions.

7.3 Live Vaccines

Avoid the use of live vaccines with AMJEVITA [see Warnings and Precautions (5.10)].

7.4 Cytochrome P450 Substrates

The formation of CYP450 enzymes may be suppressed by increased concentrations of cytokines (e.g., TNFα, IL-6) during chronic inflammation. It is possible for products that antagonize cytokine activity, such as adalimumab products, to influence the formation of CYP450 enzymes. Upon initiation or discontinuation of AMJEVITA in patients being treated with CYP450 substrates with a narrow therapeutic index, monitoring of the effect (e.g., warfarin) or drug concentration (e.g., cyclosporine or theophylline) is recommended and the individual dose of the drug product may be adjusted as needed.

8 USE IN SPECIFIC POPULATIONS

8.1 Pregnancy

Risk Summary

Available studies with use of adalimumab during pregnancy do not reliably establish an association between adalimumab and major birth defects. Clinical data are available from the Organization of Teratology Information Specialists (OTIS)/MotherToBaby Pregnancy Registry in pregnant women with rheumatoid arthritis (RA) or Crohn's disease (CD) treated with adalimumab. Registry results showed a rate of 10% for major birth defects with first trimester use of adalimumab in pregnant women with RA or CD and a rate of 7.5% for major birth defects in the disease-matched comparison cohort. The lack of pattern of major birth defects is reassuring and differences between exposure groups may have impacted the occurrence of birth defects (see Data).

Adalimumab is actively transferred across the placenta during the third trimester of pregnancy and may affect immune response in the in uteroexposed infant (see Clinical Considerations). In an embryo-fetal perinatal development study conducted in cynomolgus monkeys, no fetal harm or malformations were observed with intravenous administration of adalimumab during organogenesis and later in gestation, at doses that produced exposures up to approximately 373 times the maximum recommended human dose (MRHD) of 40 mg subcutaneous without methotrexate (see Data).

The estimated background risk of major birth defects and miscarriage for the indicated populations is unknown. All pregnancies have a background risk of birth defect, loss, or other adverse outcomes. In the U.S. general population, the estimated background risk of major birth defects and miscarriage in clinically recognized pregnancies is 2-4% and 15-20%, respectively.

Clinical Considerations

Disease-associated maternal and embryo/fetal risk

Published data suggest that the risk of adverse pregnancy outcomes in women with RA or inflammatory bowel disease (IBD) is associated with increased disease activity. Adverse pregnancy outcomes include preterm delivery (before 37 weeks of gestation), low birth weight (less than 2500 g) infants, and small for gestational age at birth.

Fetal/Neonatal Adverse Reactions

Monoclonal antibodies are increasingly transported across the placenta as pregnancy progresses, with the largest amount transferred during the third trimester [ see Data]. Risks and benefits should be considered prior to administering live or live-attenuated vaccines to infants exposed to adalimumab products in utero [see Use in Specific Populations (8.4)] .

Data

Human Data

A prospective cohort pregnancy exposure registry conducted by OTIS/MotherToBaby in the U.S. and Canada between 2004 and 2016 compared the risk of major birth defects in live-born infants of 221 women (69 RA, 152 CD) treated with adalimumab during the first trimester and 106 women (74 RA, 32 CD) not treated with adalimumab.

The proportion of major birth defects among live-born infants in the adalimumab-treated and untreated cohorts was 10% (8.7% RA, 10.5% CD) and 7.5% (6.8% RA, 9.4% CD), respectively. The lack of pattern of major birth defects is reassuring and differences between exposure groups may have impacted the occurrence of birth defects. This study cannot reliably establish whether there is an association between adalimumab and major birth defects because of methodological limitations of the registry, including small sample size, the voluntary nature of the study, and the non-randomized design.

In an independent clinical study conducted in ten pregnant women with IBD treated with adalimumab, adalimumab concentrations were measured in maternal serum as well as in cord blood (n = 10) and infant serum (n = 8) on the day of birth. The last dose of adalimumab was given between 1 and 56 days prior to delivery. Adalimumab concentrations were 0.16-19.7 mcg/mL in cord blood, 4.28-17.7 mcg/mL in infant serum, and 0-16.1 mcg/mL in maternal serum. In all but one case, the cord blood concentration of adalimumab was higher than the maternal serum concentration, suggesting adalimumab actively crosses the placenta. In addition, one infant had serum concentrations at each of the following: 6 weeks (1.94 mcg/mL), 7 weeks (1.31 mcg/mL), 8 weeks (0.93 mcg/mL), and 11 weeks (0.53 mcg/mL), suggesting adalimumab can be detected in the serum of infants exposed in uterofor at least 3 months from birth.

Animal Data

In an embryo-fetal perinatal development study, pregnant cynomolgus monkeys received adalimumab from gestation days 20 to 97 at doses that produced exposures up to 373 times that achieved with the MRHD without methotrexate (on an AUC basis with maternal IV doses up to 100 mg/kg/week). Adalimumab did not elicit harm to the fetuses or malformations.

8.2 Lactation

Risk Summary

Limited data from case reports in the published literature describe the presence of adalimumab in human milk at infant doses of 0.1% to 1% of the maternal serum concentration. Published data suggest that the systemic exposure to a breastfed infant is expected to be low because adalimumab is a large molecule and is degraded in the gastrointestinal tract. However, the effects of local exposure in the gastrointestinal tract are unknown. There are no reports of adverse effects of adalimumab products on the breastfed infant and no effects on milk production. The developmental and health benefits of breastfeeding should be considered along with the mother's clinical need for AMJEVITA and any potential adverse effects on the breastfed child from AMJEVITA or from the underlying maternal condition.

8.4 Pediatric Use

The safety and effectiveness of AMJEVITA have been established for:

- reducing signs and symptoms of moderately to severely active polyarticular JIA in pediatric patients 2 years of age and older.
- the treatment of moderately to severely active Crohn's disease in pediatric patients 6 years of age and older.

Pediatric assessments for AMJEVITA demonstrate that AMJEVITA is safe and effective for pediatric patients in indications for which HUMIRA (adalimumab) is approved. However, AMJEVITA is not approved for such indications due to marketing exclusivity for HUMIRA (adalimumab).

Due to their inhibition of TNFα, adalimumab products administered during pregnancy could affect immune response in the in utero-exposed newborn and infant. Data from eight infants exposed to adalimumab in uterosuggest adalimumab crosses the placenta [see Use in Specific Populations (8.1)] . The clinical significance of elevated adalimumab concentrations in infants is unknown. The safety of administering live or live-attenuated vaccines in exposed infants is unknown. Risks and benefits should be considered prior to vaccinating (live or live-attenuated) exposed infants.

Post-marketing cases of lymphoma, including hepatosplenic T-cell lymphoma and other malignancies, some fatal, have been reported among children, adolescents, and young adults who received treatment with TNF-blockers including adalimumab products [see Warnings and Precautions (5.2)] .

Juvenile Idiopathic Arthritis

In Study JIA-I, adalimumab was shown to reduce signs and symptoms of active polyarticular JIA in patients 4 to 17 years of age [see Clinical Studies (14.2)] . In Study JIA-II, the safety profile for patients 2 to < 4 years of age was similar to the safety profile for patients 4 to 17 years of age with polyarticular JIA [see Adverse Reactions (6.1)] . Adalimumab products have not been studied in patients with polyarticular JIA less than 2 years of age or in patients with a weight below 10 kg.

The safety of adalimumab in patients in the polyarticular JIA trials was generally similar to that observed in adults with certain exceptions [see Adverse Reactions (6.1)] .

The safety and effectiveness of adalimumab products have not been established in pediatric patients with JIA less than 2 years of age.

Pediatric Crohn's Disease

The safety and effectiveness of adalimumab products for the treatment of moderately to severely active Crohn's disease have been established in pediatric patients 6 years of age and older. Use of adalimumab products for this indication is supported by evidence from adequate and well-controlled studies in adults with additional data from a randomized, double-blind, 52-week clinical study of two dose concentrations of adalimumab in 192 pediatric patients (6 years to 17 years of age) [see Adverse Reactions (6.1), Clinical Pharmacology (12.2, 12.3), Clinical Studies (14.6)] . The adverse reaction profile in patients 6 years to 17 years of age was similar to adults.

The safety and effectiveness of adalimumab products have not been established in pediatric patients with Crohn's disease less than 6 years of age.

8.5 Geriatric Use

A total of 519 RA patients 65 years of age and older, including 107 patients 75 years of age and older, received adalimumab in clinical studies RA-I through IV. No overall difference in effectiveness was observed between these patients and younger patients. The frequency of serious infection and malignancy among adalimumab treated patients 65 years of age and older was higher than for those less than 65 years of age. Consider the benefits and risks of AMJEVITA in patients 65 years of age and older. In patients treated with AMJEVITA, closely monitor for the development of infection or malignancy [see Warnings and Precautions (5.1, 5.2)] .

10 OVERDOSAGE

Doses up to 10 mg/kg have been administered to patients in clinical trials without evidence of dose-limiting toxicities. In case of overdosage, it is recommended that the patient be monitored for any signs or symptoms of adverse reactions or effects and appropriate symptomatic treatment instituted immediately.

11 DESCRIPTION

Adalimumab-atto is a tumor necrosis factor blocker. Adalimumab-atto is a recombinant human IgG1 monoclonal antibody with human derived heavy and light chain variable regions and human IgG1:k constant regions. Adalimumab-atto is produced by recombinant DNA technology in a mammalian cell (Chinese Hamster Ovary (CHO)) expression system and is purified by a process that includes specific viral inactivation and removal steps. It consists of 1330 amino acids and has a molecular weight of approximately 148 kilodaltons.

AMJEVITA®(adalimumab-atto) injection is supplied as a sterile, preservative-free solution for subcutaneous administration. The drug product is supplied as either a single-dose, prefilled SureClick autoinjector, or as a single-dose, 1 mL prefilled glass syringe. Enclosed within the autoinjector is a single-dose, 1 mL prefilled glass syringe. The solution of AMJEVITA is clear, colorless to slightly yellow, with a pH of about 5.2.

Each 80 mg/0.8 mL prefilled syringe or prefilled autoinjector delivers 0.8 mL (80 mg) of drug product. Each 0.8 mL of AMJEVITA is formulated with L-lactic acid (1.7 mg), polysorbate 80 (0.8 mg), sodium hydroxide for pH adjustment, sucrose (67 mg), and Water for Injection, USP, pH 5.2.

Each 40 mg/0.4 mL prefilled syringe or prefilled autoinjector delivers 0.4 mL (40 mg) of drug product. Each 0.4 mL of AMJEVITA is formulated with L-lactic acid (0.9 mg), polysorbate 80 (0.4 mg), sodium hydroxide for pH adjustment, sucrose (34 mg), and Water for Injection, USP, pH 5.2.

Each 20 mg/0.2 mL prefilled syringe delivers 0.2 mL (20 mg) of drug product. Each 0.2 mL of AMJEVITA is formulated with L-lactic acid (0.4 mg), polysorbate 80 (0.2 mg), sodium hydroxide for pH adjustment, sucrose (17 mg), and Water for Injection, USP, pH 5.2.

12 CLINICAL PHARMACOLOGY

12.1 Mechanism of Action

Adalimumab products bind specifically to TNF-alpha and block its interaction with the p55 and p75 cell surface TNF receptors. Adalimumab products also lyse surface TNF expressing cells in vitroin the presence of complement. Adalimumab products do not bind or inactivate lymphotoxin (TNF-beta). TNF is a naturally occurring cytokine that is involved in normal inflammatory and immune responses. Elevated concentrations of TNF are found in the synovial fluid of patients with RA, JIA, PsA, and AS and play an important role in both the pathologic inflammation and the joint destruction that are hallmarks of these diseases. Increased concentrations of TNF are also found in psoriasis plaques. In Ps, treatment with AMJEVITA may reduce the epidermal thickness and infiltration of inflammatory cells. The relationship between these pharmacodynamic activities and the mechanism(s) by which adalimumab products exert their clinical effects is unknown.

Adalimumab products also modulate biological responses that are induced or regulated by TNF, including changes in the concentrations of adhesion molecules responsible for leukocyte migration (ELAM-1, VCAM-1, and ICAM-1 with an IC50of 1-2 × 10^-10M).

12.2 Pharmacodynamics

After treatment with adalimumab, a decrease in concentrations of acute phase reactants of inflammation (C-reactive protein [CRP] and erythrocyte sedimentation rate [ESR]) and serum cytokines (IL-6) was observed compared to baseline in patients with rheumatoid arthritis. A decrease in CRP concentrations was also observed in patients with Crohn's disease, ulcerative colitis, and hidradenitis suppurativa. Serum concentrations of matrix metalloproteinases (MMP-1 and MMP-3) that produce tissue remodeling responsible for cartilage destruction were also decreased after adalimumab administration.

12.3 Pharmacokinetics

The pharmacokinetics of adalimumab were linear over the dose range of 0.5 to 10 mg/kg following administration of a single intravenous dose (adalimumab products are not approved for intravenous use). Following 20, 40, and 80 mg every other week and every week subcutaneous administration, adalimumab mean serum trough concentrations at steady state increased approximately proportionally with dose in RA patients. The mean terminal half-life was approximately 2 weeks, ranging from 10 to 20 days across studies. Healthy subjects and patients with RA displayed similar adalimumab pharmacokinetics.

Adalimumab exposure in patients treated with 80 mg every other week is estimated to be comparable with that in patients treated with 40 mg every week.

Absorption

The average absolute bioavailability of adalimumab following a single 40 mg subcutaneous dose was 64%. The mean time to reach the maximum concentration was 5.5 days (131 ± 56 hours) and the maximum serum concentration was 4.7 ± 1.6 mcg/mL in healthy subjects following a single 40 mg subcutaneous administration of adalimumab.

Distribution

The distribution volume (Vss) ranged from 4.7 to 6.0 L following intravenous administration of doses ranging from 0.25 to 10 mg/kg in RA patients.

Elimination

The single dose pharmacokinetics of adalimumab in RA patients were determined in several studies with intravenous doses ranging from 0.25 to 10 mg/kg. The systemic clearance of adalimumab is approximately 12 mL/hr. In long-term studies with dosing more than two years, there was no evidence of changes in clearance over time in RA patients.

Patient Population

Rheumatoid Arthritis and Ankylosing Spondylitis:In patients receiving 40 mg adalimumab every other week, adalimumab mean steady-state trough concentrations were approximately 5 mcg/mL and 8 to 9 mcg/mL, without and with MTX concomitant treatment, respectively. Adalimumab concentrations in the synovial fluid from five rheumatoid arthritis patients ranged from 31 to 96% of those in serum. The pharmacokinetics of adalimumab in patients with AS were similar to those in patients with RA.

Psoriatic Arthritis:In patients receiving 40 mg every other week, adalimumab mean steady-state trough concentrations were 6 to 10 mcg/mL and 8.5 to 12 mcg/mL, without and with MTX concomitant treatment, respectively.

Plaque Psoriasis:Adalimumab mean steady-state trough concentration was approximately 5 to 6 mcg/mL during adalimumab 40 mg every other week treatment.

Adult Uveitis:Adalimumab mean steady concentration was approximately 8 to 10 mcg/mL during adalimumab 40 mg every other week treatment.

Adult Hidradenitis Suppurativa:Adalimumab trough concentrations were approximately 7 to 8 mcg/mL at Week 2 and Week 4, respectively, after receiving 160 mg on Week 0 followed by 80 mg on Week 2. Mean steady-state trough concentrations at Week 12 through Week 36 were approximately 7 to 11 mcg/mL during adalimumab 40 mg every week treatment.

Adult Crohn's Disease:Adalimumab mean trough concentrations were approximately 12 mcg/mL at Week 2 and Week 4 after receiving 160 mg on Week 0 followed by 80 mg on Week 2. Mean steady-state trough concentrations were 7 mcg/mL at Week 24 and Week 56 during adalimumab 40 mg every other week treatment.

Adult Ulcerative Colitis:Adalimumab mean trough concentrations were approximately 12 mcg/mL at Week 2 and Week 4 after receiving 160 mg on Week 0 followed by 80 mg on Week 2. Mean steady-state trough concentrations were approximately 8 mcg/mL and 15 mcg/mL at Week 52 after receiving a dose of adalimumab 40 mg every other week and 40 mg every week, respectively.

Anti-Drug Antibody Effects on Pharmacokinetics

Rheumatoid Arthritis: A trend toward higher apparent clearance of adalimumab in the presence of anti-adalimumab antibodies was identified.

Hidradenitis Suppurativa: In subjects with moderate to severe HS, antibodies to adalimumab were associated with reduced serum adalimumab concentrations. In general, the extent of reduction in serum adalimumab concentrations is greater with increasing titers of antibodies to adalimumab.

Specific Populations

Geriatric Patients:A lower clearance with increasing age was observed in patients with RA aged 40 to > 75 years.

Pediatric Patients:

Juvenile Idiopathic Arthritis:

- 4 years to 17 years of age:The adalimumab mean steady-state trough concentrations were 6.8 mcg/mL and 10.9 mcg/mL in patients weighing < 30 kg receiving 20 mg adalimumab subcutaneously every other week as monotherapy or with concomitant MTX, respectively. The adalimumab mean steady-state trough concentrations were 6.6 mcg/mL and 8.1 mcg/mL in patients weighing ≥ 30 kg receiving 40 mg adalimumab subcutaneously every other week as monotherapy or with MTX concomitant treatment, respectively.
- 2 years to < 4 years of age or 4 years of age and older weighing < 15 kg:The adalimumab mean steady-state trough adalimumab concentrations were 6.0 mcg/mL and 7.9 mcg/mL in patients receiving adalimumab subcutaneously every other week as monotherapy or with MTX concomitant treatment, respectively.

Pediatric Crohn's Disease:Adalimumab mean ± SD concentrations were 15.7±6.5 mcg/mL at Week 4 following 160 mg at Week 0 and 80 mg at Week 2, and 10.5±6.0 mcg/mL at Week 52 following 40 mg every other week dosing in patients weighing ≥ 40 kg. Adalimumab mean ± SD concentrations were 10.6±6.1 mcg/mL at Week 4 following dosing 80 mg at Week 0 and 40 mg at Week 2, and 6.9±3.6 mcg/mL at Week 52 following 20 mg every other week dosing in patients weighing < 40 kg.

Male and Female Patients:No gender-related pharmacokinetic differences were observed after correction for a patient's body weight. Healthy subjects and patients with rheumatoid arthritis displayed similar adalimumab pharmacokinetics.

Patients with Renal or Hepatic Impairment:No pharmacokinetic data are available in patients with hepatic or renal impairment.

Rheumatoid factor or CRP concentrations:Minor increases in apparent clearance were predicted in RA patients receiving doses lower than the recommended dose and in RA patients with high rheumatoid factor or CRP concentrations. These increases are not likely to be clinically important.

Drug Interaction Studies:

Methotrexate: MTX reduced adalimumab apparent clearance after single and multiple dosing by 29% and 44%, respectively, in patients with RA [see Drug Interactions (7.1)] .

13 NONCLINICAL TOXICOLOGY

13.1 Carcinogenesis, Mutagenesis, Impairment of Fertility

Long-term animal studies of adalimumab products have not been conducted to evaluate the carcinogenic potential or its effect on fertility.

14 CLINICAL STUDIES

14.1 Rheumatoid Arthritis

The efficacy and safety of adalimumab were assessed in five randomized, double-blind studies in patients ≥ 18 years of age with active rheumatoid arthritis (RA) diagnosed according to American College of Rheumatology (ACR) criteria. Patients had at least 6 swollen and 9 tender joints. Adalimumab was administered subcutaneously in combination with methotrexate (MTX) (12.5 to 25 mg, Studies RA-I, RA-III and RA-V) or as monotherapy (Studies RA-II and RA-V) or with other disease-modifying anti-rheumatic drugs (DMARDs) (Study RA-IV).

Study RA-I evaluated 271 patients who had failed therapy with at least one but no more than four DMARDs and had inadequate response to MTX. Doses of 20, 40 or 80 mg of adalimumab or placebo were given every other week for 24 weeks.

Study RA-II evaluated 544 patients who had failed therapy with at least one DMARD. Doses of placebo, 20 or 40 mg of adalimumab were given as monotherapy every other week or weekly for 26 weeks.

Study RA-III evaluated 619 patients who had an inadequate response to MTX. Patients received placebo, 40 mg of adalimumab every other week with placebo injections on alternate weeks, or 20 mg of adalimumab weekly for up to 52 weeks. Study RA-III had an additional primary endpoint at 52 weeks of inhibition of disease progression (as detected by X-ray results). Upon completion of the first 52 weeks, 457 patients enrolled in an open-label extension phase in which 40 mg of adalimumab was administered every other week for up to 5 years.

Study RA-IV assessed safety in 636 patients who were either DMARD-naive or were permitted to remain on their pre-existing rheumatologic therapy provided that therapy was stable for a minimum of 28 days. Patients were randomized to 40 mg of adalimumab or placebo every other week for 24 weeks.

Study RA-V evaluated 799 patients with moderately to severely active RA of less than 3 years duration who were ≥ 18 years old and MTX naïve. Patients were randomized to receive either MTX (optimized to 20 mg/week by week 8), adalimumab 40 mg every other week or adalimumab/MTX combination therapy for 104 weeks. Patients were evaluated for signs and symptoms, and for radiographic progression of joint damage. The median disease duration among patients enrolled in the study was 5 months. The median MTX dose achieved was 20 mg.

Clinical Response

The percent of adalimumab treated patients achieving ACR 20, 50 and 70 responses in Studies RA-II and III are shown in Table 3.

Table 3. ACR Responses in Studies RA-II and RA-III (Percent of Patients)
 | Study RA-II Monotherapy (26 weeks) |  |  | Study RA-III Methotrexate Combination (24 and 52 weeks)
Response | Placebo | Adalimumab | Adalimumab | Placebo/MTX | Adalimumab/MTX
 |  | 40 mg every other week | 40 mg weekly |  | 40 mg every other week
 | N = 110 | N = 113 | N = 103 | N = 200 | N = 207
ACR20
Month 6 | 19% | 46% [p < 0.01, adalimumab vs. placebo] | 53% | 30% | 63%
Month 12 | NA | NA | NA | 24% | 59%
ACR50
Month 6 | 8% | 22% | 35% | 10% | 39%
Month 12 | NA | NA | NA | 10% | 42%
ACR70
Month 6 | 2% | 12% | 18% | 3% | 21%
Month 12 | NA | NA | NA | 5% | 23%

The results of Study RA-I were similar to Study RA-III; patients receiving adalimumab 40 mg every other week in Study RA-I also achieved ACR 20, 50 and 70 response rates of 65%, 52% and 24%, respectively, compared to placebo responses of 13%, 7% and 3%, respectively, at 6 months (p < 0.01).

The results of the components of the ACR response criteria for Studies RA-II and RA-III are shown in Table 4. ACR response rates and improvement in all components of ACR response were maintained to week 104. Over the 2 years in Study RA-III, 20% of adalimumab patients receiving 40 mg every other week achieved a major clinical response, defined as maintenance of an ACR 70 response over a 6-month period. ACR responses were maintained in similar proportions of patients for up to 5 years with continuous adalimumab treatment in the open-label portion of Study RA-III.

Table 4. Components of ACR Response in Studies RA-II and RA-III
 | Study RA-II |  |  |  | Study RA-III
Parameter (median) | Placebo N = 110 |  | Adalimumab [40 mg adalimumab administered every other week] N = 113 |  | Placebo/MTX N = 200 |  | Adalimumab /MTX N = 207
 | Baseline | Wk 26 | Baseline | Wk 26 | Baseline | Wk 24 | Baseline | Wk 24
Number of tender joints (0-68) | 35 | 26 | 31 | 16 [p < 0.001, adalimumab vs. placebo, based on mean change from baseline] | 26 | 15 | 24 | 8
Number of swollen joints (0-66) | 19 | 16 | 18 | 10 | 17 | 11 | 18 | 5
Physician global assessment [Visual analog scale; 0 = best, 10 = worst] | 7.0 | 6.1 | 6.6 | 3.7 | 6.3 | 3.5 | 6.5 | 2.0
Patient global assessment | 7.5 | 6.3 | 7.5 | 4.5 | 5.4 | 3.9 | 5.2 | 2.0
Pain | 7.3 | 6.1 | 7.3 | 4.1 | 6.0 | 3.8 | 5.8 | 2.1
Disability index (HAQ) [Disability Index of the Health Assessment Questionnaire; 0 = best, 3 = worst, measures the patient's ability to perform the following: dress/groom, arise, eat, walk, reach, grip, maintain hygiene, and maintain daily activity] | 2.0 | 1.9 | 1.9 | 1.5 | 1.5 | 1.3 | 1.5 | 0.8
CRP (mg/dL) | 3.9 | 4.3 | 4.6 | 1.8 | 1.0 | 0.9 | 1.0 | 0.4

The time course of ACR 20 response for Study RA-III is shown in Figure 1.

In Study RA-III, 85% of patients with ACR 20 responses at week 24 maintained the response at 52 weeks. The time course of ACR 20 response for Study RA-I and Study RA-II were similar.

Figure 1. Study RA-III ACR 20 Responses over 52 Weeks

In Study RA-IV, 53% of patients treated with adalimumab 40 mg every other week plus standard of care had an ACR 20 response at week 24 compared to 35% on placebo plus standard of care (p < 0.001). No unique adverse reactions related to the combination of adalimumab and other DMARDs were observed.

In Study RA-V with MTX naïve patients with recent onset RA, the combination treatment with adalimumab plus MTX led to greater percentages of patients achieving ACR responses than either MTX monotherapy or adalimumab monotherapy at Week 52 and responses were sustained at Week 104 (see Table 5).

Table 5. ACR Response in Study RA-V (Percent of Patients)
Response | MTX [p < 0.05, Adalimumab/MTX vs. MTX for ACR 20 p < 0.001, Adalimumab/MTX vs. MTX for ACR 50 and 70, and Major Clinical Response] N = 257 | Adalimumab [p < 0.001, Adalimumab/MTX vs. Adalimumab] N = 274 | Adalimumab/MTX N = 268
ACR20
Week 52 | 63% | 54% | 73%
Week 104 | 56% | 49% | 69%
ACR50
Week 52 | 46% | 41% | 62%
Week 104 | 43% | 37% | 59%
ACR70
Week 52 | 27% | 26% | 46%
Week 104 | 28% | 28% | 47%
Major Clinical Response [Major clinical response is defined as achieving an ACR 70 response for a continuous six-month period] | 28% | 25% | 49%

At Week 52, all individual components of the ACR response criteria for Study RA-V improved in the adalimumab/MTX group and improvements were maintained to Week 104.

Radiographic Response

In Study RA-III, structural joint damage was assessed radiographically and expressed as change in Total Sharp Score (TSS) and its components, the erosion score and Joint Space Narrowing (JSN) score, at month 12 compared to baseline. At baseline, the median TSS was approximately 55 in the placebo and 40 mg every other week groups. The results are shown in Table 6. Adalimumab/MTX treated patients demonstrated less radiographic progression than patients receiving MTX alone at 52 weeks.

Table 6. Radiographic Mean Changes Over 12 Months in Study RA-III
 | Placebo/MTX | Adalimumab/MTX 40 mg every other week | Placebo/MTX-Adalimumab/MTX (95% Confidence Interval [95% confidence intervals for the differences in change scores between MTX and adalimumab.]) | P-value [Based on rank analysis]
Total Sharp score | 2.7 | 0.1 | 2.6 (1.4, 3.8) | < 0.001
Erosion score | 1.6 | 0.0 | 1.6 (0.9, 2.2) | < 0.001
JSN score | 1.0 | 0.1 | 0.9 (0.3, 1.4) | 0.002

In the open-label extension of Study RA-III, 77% of the original patients treated with any dose of adalimumab were evaluated radiographically at 2 years. Patients maintained inhibition of structural damage, as measured by the TSS. Fifty-four percent (54%) had no progression of structural damage as defined by a change in the TSS of zero or less. Fifty-five percent (55%) of patients originally treated with 40 mg adalimumab every other week have been evaluated radiographically at 5 years. Patients had continued inhibition of structural damage with 50% showing no progression of structural damage defined by a change in the TSS of zero or less.

In Study RA-V, structural joint damage was assessed as in Study RA-III. Greater inhibition of radiographic progression, as assessed by changes in TSS, erosion score and JSN was observed in the adalimumab/MTX combination group as compared to either the MTX or adalimumab monotherapy group at Week 52 as well as at Week 104 (see Table 7).

Table 7. Radiographic Mean Change [mean (95% confidence interval)] in Study RA-V
 |  | MTX [p < 0.001, adalimumab/MTX vs. MTX at 52 and 104 weeks and for adalimumab /MTX vs. adalimumab at 104 weeks] N = 257 | Adalimumab , [p < 0.01, for adalimumab/MTX vs. adalimumab at 52 weeks] N = 274 | Adalimumab/MTX N = 268
52 Weeks | Total Sharp score | 5.7 (4.2, 7.3) | 3.0 (1.7, 4.3) | 1.3 (0.5, 2.1)
 | Erosion score | 3.7 (2.7, 4.8) | 1.7 (1.0, 2.4) | 0.8 (0.4, 1.2)
 | JSN score | 2.0 (1.2, 2.8) | 1.3 (0.5, 2.1) | 0.5 (0.0, 1.0)
104 Weeks | Total Sharp score | 10.4 (7.7, 13.2) | 5.5 (3.6, 7.4) | 1.9 (0.9, 2.9)
 | Erosion score | 6.4 (4.6, 8.2) | 3.0 (2.0, 4.0) | 1.0 (0.4, 1.6)
 | JSN score | 4.1 (2.7, 5.4) | 2.6 (1.5, 3.7) | 0.9 (0.3, 1.5)

Physical Function Response

In studies RA-I through IV, adalimumab showed significantly greater improvement than placebo in the disability index of Health Assessment Questionnaire (HAQ-DI) from baseline to the end of study, and significantly greater improvement than placebo in the health-outcomes as assessed by The Short Form Health Survey (SF 36). Improvement was seen in both the Physical Component Summary (PCS) and the Mental Component Summary (MCS).

In Study RA-III, the mean (95% CI) improvement in HAQ-DI from baseline at week 52 was 0.60 (0.55, 0.65) for the adalimumab patients and 0.25 (0.17, 0.33) for placebo/MTX (p < 0.001) patients. Sixty-three percent of adalimumab-treated patients achieved a 0.5 or greater improvement in HAQ-DI at week 52 in the double-blind portion of the study. Eighty-two percent of these patients maintained that improvement through week 104 and a similar proportion of patients maintained this response through week 260 (5 years) of open-label treatment. Mean improvement in the SF-36 was maintained through the end of measurement at week 156 (3 years).

In Study RA-V, the HAQ-DI and the physical component of the SF-36 showed greater improvement (p < 0.001) for the adalimumab/MTX combination therapy group versus either the MTX monotherapy or the adalimumab monotherapy group at Week 52, which was maintained through Week 104.

14.2 Juvenile Idiopathic Arthritis

The safety and efficacy of adalimumab was assessed in two studies (Studies JIA-I and JIA-II) in patients with active polyarticular juvenile idiopathic arthritis (JIA).

Study JIA-I

The safety and efficacy of adalimumab were assessed in a multicenter, randomized, withdrawal, double-blind, parallel-group study in 171 patients who were 4 to 17 years of age with polyarticular JIA. In the study, the patients were stratified into two groups: MTX-treated or non-MTX-treated. All patients had to show signs of active moderate or severe disease despite previous treatment with NSAIDs, analgesics, corticosteroids, or DMARDs. Patients who received prior treatment with any biologic DMARDs were excluded from the study.

The study included four phases: an open-label lead in phase (OL-LI; 16 weeks), a double-blind randomized withdrawal phase (DB; 32 weeks), an open-label extension phase (OLE-BSA; up to 136 weeks), and an open-label fixed dose phase (OLE-FD; 16 weeks). In the first three phases of the study, adalimumab was administered based on body surface area at a dose of 24 mg/m^2up to a maximum total body dose of 40 mg subcutaneously (SC) every other week. In the OLE-FD phase, the patients were treated with 20 mg of adalimumab SC every other week if their weight was less than 30 kg and with 40 mg of adalimumab SC every other week if their weight was 30 kg or greater. Patients remained on stable doses of NSAIDs and or prednisone (≤ 0.2 mg/kg/day or 10 mg/day maximum).

Patients demonstrating a Pediatric ACR 30 response at the end of OL-LI phase were randomized into the double blind (DB) phase of the study and received either adalimumab or placebo every other week for 32 weeks or until disease flare. Disease flare was defined as a worsening of ≥ 30% from baseline in ≥ 3 of 6 Pediatric ACR core criteria, ≥ 2 active joints, and improvement of > 30% in no more than 1 of the 6 criteria. After 32 weeks or at the time of disease flare during the DB phase, patients were treated in the open-label extension phase based on the BSA regimen (OLE-BSA), before converting to a fixed dose regimen based on body weight (OLE-FD phase).

Study JIA-I Clinical Response

At the end of the 16-week OL-LI phase, 94% of the patients in the MTX stratum and 74% of the patients in the non-MTX stratum were Pediatric ACR 30 responders. In the DB phase significantly fewer patients who received adalimumab experienced disease flare compared to placebo, both without MTX (43% vs.71%) and with MTX (37% vs.65%). More patients treated with adalimumab continued to show pediatric ACR 30/50/70 responses at Week 48 compared to patients treated with placebo. Pediatric ACR responses were maintained for up to two years in the OLE phase in patients who received adalimumab throughout the study.

Study JIA-II

Adalimumab was assessed in an open-label, multicenter study in 32 patients who were 2 to < 4 years of age or 4 years of age and older weighing < 15 kg with moderately to severely active polyarticular JIA. Most patients (97%) received at least 24 weeks of adalimumab treatment dosed 24 mg/m^2up to a maximum of 20 mg every other week as a single SC injection up to a maximum of 120 weeks duration. During the study, most patients used concomitant MTX, with fewer reporting use of corticosteroids or NSAIDs. The primary objective of the study was evaluation of safety [see Adverse Reactions (6.1)] .

14.3 Psoriatic Arthritis

The safety and efficacy of adalimumab was assessed in two randomized, double-blind, placebo-controlled studies in 413 patients with psoriatic arthritis (PsA). Upon completion of both studies, 383 patients enrolled in an open-label extension study, in which 40 mg adalimumab was administered every other week.

Study PsA-I enrolled 313 adult patients with moderately to severely active PsA (> 3 swollen and > 3 tender joints) who had an inadequate response to NSAID therapy in one of the following forms: (1) distal interphalangeal (DIP) involvement (N = 23); (2) polyarticular arthritis (absence of rheumatoid nodules and presence of plaque psoriasis) (N = 210); (3) arthritis mutilans (N = 1); (4) asymmetric PsA (N = 77); or (5) AS-like (N = 2). Patients on MTX therapy (158 of 313 patients) at enrollment (stable dose of ≤ 30 mg/week for > 1 month) could continue MTX at the same dose. Doses of adalimumab 40 mg or placebo every other week were administered during the 24-week double-blind period of the study.

Compared to placebo, treatment with adalimumab resulted in improvements in the measures of disease activity (see Tables 8and 9). Among patients with PsA who received adalimumab, the clinical responses were apparent in some patients at the time of the first visit (two weeks) and were maintained up to 88 weeks in the ongoing open-label study. Similar responses were seen in patients with each of the subtypes of psoriatic arthritis, although few patients were enrolled with the arthritis mutilans and ankylosing spondylitis-like subtypes. Responses were similar in patients who were or were not receiving concomitant MTX therapy at baseline.

Patients with psoriatic involvement of at least three percent body surface area (BSA) were evaluated for Psoriatic Area and Severity Index (PASI) responses. At 24 weeks, the proportions of patients achieving a 75% or 90% improvement in the PASI were 59% and 42%, respectively, in the adalimumab group (N = 69), compared to 1% and 0%, respectively, in the placebo group (N = 69) (p < 0.001). PASI responses were apparent in some patients at the time of the first visit (two weeks). Responses were similar in patients who were or were not receiving concomitant MTX therapy at baseline.

Table 8. ACR Response in Study PsA-I (Percent of Patients)
 | Placebo N = 162 | Adalimumab [p < 0.001 for all comparisons between adalimumab and placebo] N = 151
ACR 20
Week 12 | 14% | 58%
Week 24 | 15% | 57%
ACR 50
Week 12 | 4% | 36%
Week 24 | 6% | 39%
ACR 70
Week 12 | 1% | 20%
Week 24 | 1% | 23%

Table 9. Components of Disease Activity in Study PsA-I
 | Placebo N = 162 |  | Adalimumab [p < 0.001 for adalimumab vs. placebo comparisons based on median changes] N = 151
Parameter: median | Baseline | 24 weeks | Baseline | 24 weeks
Number of tender joints [Scale 0-78] | 23.0 | 17.0 | 20.0 | 5.0
Number of swollen joints [Scale 0-76] | 11.0 | 9.0 | 11.0 | 3.0
Physician global assessment [Visual analog scale; 0 = best, 100 = worst] | 53.0 | 49.0 | 55.0 | 16.0
Patient global assessment | 49.5 | 49.0 | 48.0 | 20.0
Pain | 49.0 | 49.0 | 54.0 | 20.0
Disability index (HAQ) [Disability Index of the Health Assessment Questionnaire; 0 = best, 3 = worst; measures the patient's ability to perform the following: dress/groom, arise, eat, walk, reach, grip, maintain hygiene, and maintain daily activity] | 1.0 | 0.9 | 1.0 | 0.4
CRP (mg/dL) [Normal range: 0-0.287 mg/dL] | 0.8 | 0.7 | 0.8 | 0.2

Similar results were seen in an additional, 12-week study in 100 patients with moderate to severe psoriatic arthritis who had suboptimal response to DMARD therapy as manifested by ≥ 3 tender joints and ≥ 3 swollen joints at enrollment.

Radiographic Response

Radiographic changes were assessed in the PsA studies. Radiographs of hands, wrists, and feet were obtained at baseline and Week 24 during the double-blind period when patients were on adalimumab or placebo and at Week 48 when all patients were on open-label adalimumab. A modified Total Sharp Score (mTSS), which included distal interphalangeal joints (i.e., not identical to the TSS used for rheumatoid arthritis), was used by readers blinded to treatment group to assess the radiographs.

Adalimumab-treated patients demonstrated greater inhibition of radiographic progression compared to placebo-treated patients and this effect was maintained at 48 weeks (see Table 10).

Table 10. Change in Modified Total Sharp Score in Psoriatic Arthritis
 | Placebo N = 141 | Adalimumab N = 133
 | Week 24 | Week 24 | Week 48
Baseline mean | 22.1 | 23.4 | 23.4
Mean Change ± SD | 0.9 ± 3.1 | -0.1 ± 1.7 | -0.2 ± 4.9 [< 0.001 for the difference between adalimumab, Week 48 and Placebo, Week 24 (primary analysis)]

Physical Function Response

In Study PsA-I, physical function and disability were assessed using the HAQ Disability Index (HAQ-DI) and the SF-36 Health Survey. Patients treated with 40 mg of adalimumab every other week showed greater improvement from baseline in the HAQ-DI score (mean decreases of 47% and 49% at Weeks 12 and 24, respectively) in comparison to placebo (mean decreases of 1% and 3% at Weeks 12 and 24, respectively). At Weeks 12 and 24, patients treated with adalimumab showed greater improvement from baseline in the SF-36 Physical Component Summary score compared to patients treated with placebo, and no worsening in the SF-36 Mental Component Summary score. Improvement in physical function based on the HAQ-DI was maintained for up to 84 weeks through the open-label portion of the study.

14.4 Ankylosing Spondylitis

The safety and efficacy of adalimumab 40 mg every other week was assessed in 315 adult patients in a randomized, 24 week double-blind, placebo-controlled study in patients with active ankylosing spondylitis (AS) who had an inadequate response to glucocorticoids, NSAIDs, analgesics, methotrexate or sulfasalazine. Active AS was defined as patients who fulfilled at least two of the following three criteria: (1) a Bath AS disease activity index (BASDAI) score ≥ 4 cm, (2) a visual analog score (VAS) for total back pain ≥ 40 mm, and (3) morning stiffness ≥ 1 hour. The blinded period was followed by an open-label period during which patients received adalimumab 40 mg every other week subcutaneously for up to an additional 28 weeks.

Improvement in measures of disease activity was first observed at Week 2 and maintained through 24 weeks as shown in Figure 2 and Table 11.

Responses of patients with total spinal ankylosis (n = 11) were similar to those without total ankylosis.

Figure 2. ASAS 20 Response By Visit, Study AS-I

At 12 weeks, the ASAS 20/50/70 responses were achieved by 58%, 38%, and 23%, respectively, of patients receiving adalimumab, compared to 21%, 10%, and 5%, respectively, of patients receiving placebo (p < 0.001). Similar responses were seen at Week 24 and were sustained in patients receiving open-label adalimumab for up to 52 weeks.

A greater proportion of patients treated with adalimumab (22%) achieved a low level of disease activity at 24 weeks (defined as a value < 20 [on a scale of 0 to 100 mm] in each of the four ASAS response parameters) compared to patients treated with placebo (6%).

Table 11. Components of Ankylosing Spondylitis Disease Activity
 | Placebo N = 107 |  | Adalimumab N = 208
 | Baseline mean | Week 24 mean | Baseline mean | Week 24 mean
ASAS 20 Response Criteria [statistically significant for comparisons between adalimumab and placebo at Week 24]
Patient's Global Assessment of Disease Activity [Percent of subjects with at least a 20% and 10-unit improvement measured on a Visual Analog Scale (VAS) with 0 = "none" and 100 = "severe"] | 65 | 60 | 63 | 38
Total back pain | 67 | 58 | 65 | 37
Inflammation [mean of questions 5 and 6 of BASDAI (defined in 'd')] | 6.7 | 5.6 | 6.7 | 3.6
BASFI [Bath Ankylosing Spondylitis Functional Index] | 56 | 51 | 52 | 34
BASDAI [Bath Ankylosing Spondylitis Disease Activity Index] score | 6.3 | 5.5 | 6.3 | 3.7
BASMI [Bath Ankylosing Spondylitis Metrology Index] score | 4.2 | 4.1 | 3.8 | 3.3
Tragus to wall (cm) | 15.9 | 15.8 | 15.8 | 15.4
Lumbar flexion (cm) | 4.1 | 4.0 | 4.2 | 4.4
Cervical rotation (degrees) | 42.2 | 42.1 | 48.4 | 51.6
Lumbar side flexion (cm) | 8.9 | 9.0 | 9.7 | 11.7
Intermalleolar distance (cm) | 92.9 | 94.0 | 93.5 | 100.8
CRP [C-Reactive Protein (mg/dL)] | 2.2 | 2.0 | 1.8 | 0.6

A second randomized, multicenter, double-blind, placebo-controlled study of 82 patients with ankylosing spondylitis showed similar results.

Patients treated with adalimumab achieved improvement from baseline in the Ankylosing Spondylitis Quality of Life Questionnaire (ASQoL) score (-3.6 vs.-1.1) and in the Short Form Health Survey (SF-36) Physical Component Summary (PCS) score (7.4 vs.1.9) compared to placebo-treated patients at Week 24.

14.5 Adult Crohn's Disease

The safety and efficacy of multiple doses of adalimumab were assessed in adult patients with moderately to severely active Crohn's disease, CD, (Crohn's Disease Activity Index (CDAI) ≥ 220 and ≤ 450) in randomized, double-blind, placebo-controlled studies. Concomitant stable doses of aminosalicylates, corticosteroids, and/or immunomodulatory agents were permitted, and 79% of patients continued to receive at least one of these medications.

Induction of clinical remission (defined as CDAI < 150) was evaluated in two studies. In Study CD-I, 299 TNF-blocker naïve patients were randomized to one of four treatment groups: the placebo group received placebo at Weeks 0 and 2, the 160/80 group received 160 mg adalimumab at Week 0 and 80 mg at Week 2, the 80/40 group received 80 mg at Week 0 and 40 mg at Week 2, and the 40/20 group received 40 mg at Week 0 and 20 mg at Week 2. Clinical results were assessed at Week 4.

In the second induction study, Study CD-II, 325 patients who had lost response to, or were intolerant to, previous infliximab therapy were randomized to receive either 160 mg adalimumab at Week 0 and 80 mg at Week 2, or placebo at Weeks 0 and 2. Clinical results were assessed at Week 4.

Maintenance of clinical remission was evaluated in Study CD-III. In this study, 854 patients with active disease received open-label adalimumab, 80 mg at week 0 and 40 mg at Week 2. Patients were then randomized at Week 4 to 40 mg adalimumab every other week, 40 mg adalimumab every week, or placebo. The total study duration was 56 weeks. Patients in clinical response (decrease in CDAI ≥ 70) at Week 4 were stratified and analyzed separately from those not in clinical response at Week 4.

Induction of Clinical Remission

A greater percentage of the patients treated with 160/80 mg adalimumab achieved induction of clinical remission versus placebo at Week 4 regardless of whether the patients were TNF-blocker naïve (CD-I), or had lost response to or were intolerant to infliximab (CD-II) (see Table 12).

Table 12. Induction of Clinical Remission in Studies CD-I and CD-II (Percent of Patients)
 | CD-I |  | CD-II
 | Placebo N = 74 | Adalimumab 160/80 mg N = 76 | Placebo N = 166 | Adalimumab 160/80 mg N = 159
Week 4
Clinical remission | 12% | 36% [p < 0.001 for adalimumab vs. placebo pairwise comparison of proportions] | 7% | 21%
Clinical response | 34% | 58% [p < 0.01 for adalimumab vs. placebo pairwise comparison of proportions] | 34% | 52%
Clinical remission is CDAI score < 150; clinical response is decrease in CDAI of at least 70 points.

Maintenance of Clinical Remission

In Study CD-III at Week 4, 58% (499/854) of patients were in clinical response and were assessed in the primary analysis. At Weeks 26 and 56, greater proportions of patients who were in clinical response at Week 4 achieved clinical remission in the adalimumab 40 mg every other week maintenance group compared to patients in the placebo maintenance group (see Table 13). The group that received adalimumab therapy every week did not demonstrate significantly higher remission rates compared to the group that received adalimumab every other week.

Table 13. Maintenance of Clinical Remission in CD-III (Percent of Patients)
 | Placebo | 40 mg Adalimumab every other week
 | N = 170 | N = 172
Week 26
Clinical remission | 17% | 40% [p < 0.001 for adalimumab vs. placebo pairwise comparisons of proportions]
Clinical response | 28% | 54%
Week 56
Clinical remission | 12% | 36%
Clinical response | 18% | 43%
Clinical remission is CDAI score < 150; clinical response is decrease in CDAI of at least 70 points.

Of those in response at Week 4 who attained remission during the study, patients in the adalimumab every other week group maintained remission for a longer time than patients in the placebo maintenance group. Among patients who were not in response by Week 12, therapy continued beyond 12 weeks did not result in significantly more responses.

14.6 Pediatric Crohn's Disease

A randomized, double-blind, 52-week clinical study of 2 dose concentrations of adalimumab (Study PCD-I) was conducted in 192 pediatric patients (6 to 17 years of age) with moderately to severely active Crohn's disease (defined as Pediatric Crohn's Disease Activity Index (PCDAI) score > 30). Enrolled patients had over the previous two year period an inadequate response to corticosteroids or an immunomodulator (i.e., azathioprine, 6-mercaptopurine, or methotrexate). Patients who had previously received a TNF-blocker were allowed to enroll if they had previously had loss of response or intolerance to that TNF-blocker.

Patients received open-label induction therapy at a dose based on their body weight (≥ 40 kg and < 40 kg). Patients weighing ≥ 40 kg received 160 mg (at Week 0) and 80 mg (at Week 2). Patients weighing < 40 kg received 80 mg (at Week 0) and 40 mg (at Week 2). At Week 4, patients within each body weight category (≥ 40 kg and < 40 kg) were randomized 1:1 to one of two maintenance dose regimens (high dose and low dose). The high dose was 40 mg every other week for patients weighing ≥ 40 kg and 20 mg every other week for patients weighing < 40 kg. The low dose was 20 mg every other week for patients weighing ≥ 40 kg and 10 mg every other week for patients weighing < 40 kg.

Concomitant stable dosages of corticosteroids (prednisone dosage ≤ 40 mg/day or equivalent) and immunomodulators (azathioprine, 6-mercaptopurine, or methotrexate) were permitted throughout the study.

At Week 12, patients who experienced a disease flare (increase in PCDAI of ≥ 15 from Week 4 and absolute PCDAI > 30) or who were non-responders (did not achieve a decrease in the PCDAI of ≥ 15 from baseline for 2 consecutive visits at least 2 weeks apart) were allowed to dose-escalate (i.e., switch from blinded every other week dosing to blinded every week dosing); patients who dose-escalated were considered treatment failures.

At baseline, 38% of patients were receiving corticosteroids, and 62% of patients were receiving an immunomodulator. Forty-four percent (44%) of patients had previously lost response or were intolerant to a TNF-blocker. The median baseline PCDAI score was 40.

Of the 192 patients total, 188 patients completed the 4 week induction period, 152 patients completed 26 weeks of treatment, and 124 patients completed 52 weeks of treatment. Fifty-one percent (51%) (48/95) of patients in the low maintenance dose group dose-escalated, and 38% (35/93) of patients in the high maintenance dose group dose-escalated.

At Week 4, 28% (52/188) of patients were in clinical remission (defined as PCDAI ≤ 10).

The proportions of patients in clinical remission (defined as PCDAI ≤ 10) and clinical response (defined as reduction in PCDAI of at least 15 points from baseline) were assessed at Weeks 26 and 52.

At both Weeks 26 and 52, the proportion of patients in clinical remission and clinical response was numerically higher in the high dose group compared to the low dose group (see Table 14). The recommended maintenance regimen is 20 mg every other week for patients weighing < 40 kg and 40 mg every other week for patients weighing ≥ 40 kg. Every week dosing is not the recommended maintenance dosing regimen [see Dosage and Administration (2.3)] .

Table 14. Clinical Remission and Clinical Response in Study PCD-I
 | Low Maintenance Dose [The low maintenance dose was 20 mg every other week for patients weighing ≥ 40 kg and 10 mg every other week for patients weighing < 40 kg.] (20 or 10 mg every other week) N = 95 | High Maintenance Dose [The high maintenance dose was 40 mg every other week for patients weighing ≥ 40 kg and 20 mg every other week for patients weighing < 40 kg.] (40 or 20 mg every other week) N = 93
Week 26
Clinical remission [Clinical remission defined as PCDAI ≤ 10.] | 28% | 39%
Clinical response [Clinical response defined as reduction in PCDAI of at least 15 points from baseline.] | 48% | 59%
Week 52
Clinical remission | 23% | 33%
Clinical response | 28% | 42%

14.7 Adult Ulcerative Colitis

The safety and efficacy of adalimumab were assessed in adult patients with moderately to severely active ulcerative colitis (Mayo score 6 to 12 on a 12 point scale, with an endoscopy subscore of 2 to 3 on a scale of 0 to 3) despite concurrent or prior treatment with immunosuppressants such as corticosteroids, azathioprine, or 6-MP in two randomized, double-blind, placebo-controlled clinical studies (Studies UC-I and UC-II). Both studies enrolled TNF-blocker naïve patients, but Study UC-II also allowed entry of patients who lost response to or were intolerant to TNF-blockers. Forty percent (40%) of patients enrolled in Study UC-II had previously used another TNF-blocker.

Concomitant stable doses of aminosalicylates and immunosuppressants were permitted. In Studies UC-I and II, patients were receiving aminosalicylates (69%), corticosteroids (59%) and/or azathioprine or 6-MP (37%) at baseline. In both studies, 92% of patients received at least one of these medications.

Induction of clinical remission (defined as Mayo score ≤ 2 with no individual subscores > 1) at Week 8 was evaluated in both studies. Clinical remission at Week 52 and sustained clinical remission (defined as clinical remission at both Weeks 8 and 52) were evaluated in Study UC-II.

In Study UC-I, 390 TNF-blocker naïve patients were randomized to one of three treatment groups for the primary efficacy analysis. The placebo group received placebo at Weeks 0, 2, 4 and 6. The 160/80 group received 160 mg adalimumab at Week 0 and 80 mg at Week 2, and the 80/40 group received 80 mg adalimumab at Week 0 and 40 mg at Week 2. After Week 2, patients in both adalimumab treatment groups received 40 mg every other week.

In Study UC-II, 518 patients were randomized to receive either adalimumab 160 mg at Week 0, 80 mg at Week 2, and 40 mg every other week starting at Week 4 through Week 50, or placebo starting at Week 0 and every other week through Week 50. Corticosteroid taper was permitted starting at Week 8.

In both Studies UC-I and UC-II, a greater percentage of the patients treated with 160/80 mg of adalimumab compared to patients treated with placebo achieved induction of clinical remission. In Study UC-II, a greater percentage of the patients treated with 160/80 mg of adalimumab compared to patients treated with placebo achieved sustained clinical remission (clinical remission at both Weeks 8 and 52) (see Table 15).

Table 15. Induction of Clinical Remission in Studies UC-I and UC-II and Sustained Clinical Remission in Study UC-II (Percent of Patients)
 | Study UC-I |  |  | Study UC-II
 | Placebo N = 130 | Adalimumab 160/80 mg N = 130 | Treatment Difference (95% CI) | Placebo N = 246 | Adalimumab 160/80 mg N = 248 | Treatment Difference (95% CI)
Induction of Clinical Remission (Clinical Remission at Week 8) | 9.2% | 18.5% | 9.3% [p < 0.05 for adalimumab vs. placebo pairwise comparison of proportions] (0.9%, 17.6%) | 9.3% | 16.5% | 7.2% (1.2%, 12.9%)
Sustained Clinical Remission (Clinical Remission at both Weeks 8 and 52) | N/A | N/A | N/A | 4.1% | 8.5% | 4.4% (0.1%, 8.6%)
Clinical remission is defined as Mayo score ≤ 2 with no individual subscores > 1.
CI = Confidence interval

In Study UC-I, there was no statistically significant difference in clinical remission observed between the adalimumab 80/40 mg group and the placebo group at Week 8.

In Study UC-II, 17.3% (43/248) in the adalimumab group were in clinical remission at Week 52 compared to 8.5% (21/246) in the placebo group (treatment difference: 8.8%; 95% confidence interval (CI): [2.8%, 14.5%]; p < 0.05).

In the subgroup of patients in Study UC-II with prior TNF-blocker use, the treatment difference for induction of clinical remission appeared to be lower than that seen in the whole study population, and the treatment differences for sustained clinical remission and clinical remission at Week 52 appeared to be similar to those seen in the whole study population. The subgroup of patients with prior TNF-blocker use achieved induction of clinical remission at 9% (9/98) in the adalimumab group versus 7% (7/101) in the placebo group, and sustained clinical remission at 5% (5/98) in the adalimumab group versus 1% (1/101) in the placebo group. In the subgroup of patients with prior TNF-blocker use, 10% (10/98) were in clinical remission at Week 52 in the adalimumab group versus 3% (3/101) in the placebo group.

14.8 Plaque Psoriasis

The safety and efficacy of adalimumab were assessed in randomized, double-blind, placebo-controlled studies in 1696 adult subjects with moderate to severe chronic plaque psoriasis (Ps) who were candidates for systemic therapy or phototherapy.

Study Ps-I evaluated 1212 subjects with chronic Ps with ≥ 10% body surface area (BSA) involvement, Physician's Global Assessment (PGA) of at least moderate disease severity, and Psoriasis Area and Severity Index (PASI) ≥ 12 within three treatment periods. In period A, subjects received placebo or adalimumab at an initial dose of 80 mg at Week 0 followed by a dose of 40 mg every other week starting at Week 1. After 16 weeks of therapy, subjects who achieved at least a PASI 75 response at Week 16, defined as a PASI score improvement of at least 75% relative to baseline, entered period B and received open-label 40 mg adalimumab every other week. After 17 weeks of open-label therapy, subjects who maintained at least a PASI 75 response at Week 33 and were originally randomized to active therapy in period A were re-randomized in period C to receive 40 mg adalimumab every other week or placebo for an additional 19 weeks. Across all treatment groups the mean baseline PASI score was 19 and the baseline Physician's Global Assessment score ranged from "moderate" (53%) to "severe" (41%) to "very severe" (6%).

Study Ps-II evaluated 99 subjects randomized to adalimumab and 48 subjects randomized to placebo with chronic plaque psoriasis with ≥ 10% BSA involvement and PASI ≥ 12. Subjects received placebo, or an initial dose of 80 mg adalimumab at Week 0 followed by 40 mg every other week starting at Week 1 for 16 weeks. Across all treatment groups the mean baseline PASI score was 21 and the baseline PGA score ranged from "moderate" (41%) to "severe" (51%) to "very severe" (8%).

Studies Ps-I and II evaluated the proportion of subjects who achieved "clear" or "minimal" disease on the 6-point PGA scale and the proportion of subjects who achieved a reduction in PASI score of at least 75% (PASI 75) from baseline at Week 16 (see Table 16and 17).

Additionally, Study Ps-I evaluated the proportion of subjects who maintained a PGA of "clear" or "minimal" disease or a PASI 75 response after Week 33 and on or before Week 52.

Table 16. Efficacy Results at 16 Weeks in Study Ps-I Number of Subjects (%)
 | Adalimumab 40 mg every other week | Placebo
 | N = 814 | N = 398
PGA: Clear or minimal [Clear = no plaque elevation, no scale, plus or minus hyperpigmentation or diffuse pink or red coloration Minimal = possible but difficult to ascertain whether there is slight elevation of plaque above normal skin, plus or minus surface dryness with some white coloration, plus or minus up to red coloration] | 506 (62%) | 17 (4%)
PASI 75 | 578 (71%) | 26 (7%)

Table 17. Efficacy Results at 16 Weeks in Study Ps-II Number of Subjects (%)
 | Adalimumab 40 mg every other week | Placebo
 | N = 99 | N = 48
PGA: Clear or minimal [Clear = no plaque elevation, no scale, plus or minus hyperpigmentation or diffuse pink or red coloration Minimal = possible but difficult to ascertain whether there is slight elevation of plaque above normal skin, plus or minus surface dryness with some white coloration, plus or minus up to red coloration] | 70 (71%) | 5 (10%)
PASI 75 | 77 (78%) | 9 (19%)

Additionally, in Study Ps-I, subjects on adalimumab who maintained a PASI 75 were re-randomized to adalimumab (N = 250) or placebo (N = 240) at Week 33. After 52 weeks of treatment with adalimumab, more subjects on adalimumab maintained efficacy when compared to subjects who were re-randomized to placebo based on maintenance of PGA of "clear" or "minimal" disease (68% vs.28%) or a PASI 75 (79% vs.43%).

A total of 347 stable responders participated in a withdrawal and retreatment evaluation in an open-label extension study. Median time to relapse (decline to PGA "moderate" or worse) was approximately 5 months. During the withdrawal period, no subject experienced transformation to either pustular or erythrodermic psoriasis. A total of 178 subjects who relapsed re-initiated treatment with 80 mg of adalimumab, then 40 mg every other week beginning at week 1. At week 16, 69% (123/178) of subjects had a response of PGA "clear" or "minimal".

A randomized, double-blind study (Study Ps-III) compared the efficacy and safety of adalimumab versus placebo in 217 adult subjects. Subjects in the study had to have chronic plaque psoriasis of at least moderate severity on the PGA scale, fingernail involvement of at least moderate severity on a 5-point Physician's Global Assessment of Fingernail Psoriasis (PGA-F) scale, a Modified Nail Psoriasis Severity Index (mNAPSI) score for the target-fingernail of ≥ 8, and either a BSA involvement of at least 10% or a BSA involvement of at least 5% with a total mNAPSI score for all fingernails of ≥ 20. Subjects received an initial dose of 80 mg adalimumab followed by 40 mg every other week (starting one week after the initial dose) or placebo for 26 weeks followed by open-label adalimumab treatment for an additional 26 weeks. This study evaluated the proportion of subjects who achieved "clear" or "minimal" assessment with at least a 2-grade improvement on the PGA-F scale and the proportion of subjects who achieved at least a 75% improvement from baseline in the mNAPSI score (mNAPSI 75) at Week 26.

At Week 26, a higher proportion of subjects in the adalimumab group than in the placebo group achieved the PGA-F endpoint. Furthermore, a higher proportion of subjects in the adalimumab group than in the placebo group achieved mNAPSI 75 at Week 26 (see Table 18).

Table 18. Efficacy Results at 26 Weeks
Endpoint | Adalimumab 40 mg every other week [Subjects received 80 mg of adalimumab at Week 0, followed by 40 mg every other week starting at Week 1.] N = 109 | Placebo N = 108
PGA-F: ≥ 2-grade improvement and clear or minimal | 49% | 7%
mNAPSI 75 | 47% | 3%

Nail pain was also evaluated and improvement in nail pain was observed in Study Ps-III.

14.9 Hidradenitis Suppurativa

Two randomized, double-blind, placebo-controlled studies (Studies HS-I and II) evaluated the safety and efficacy of adalimumab in a total of 633 adult subjects with moderate to severe hidradenitis suppurativa (HS) with Hurley Stage II or III disease and with at least 3 abscesses or inflammatory nodules.

In both studies, subjects received placebo or adalimumab at an initial dose of 160 mg at Week 0, 80 mg at Week 2, and 40 mg every week starting at Week 4 and continued through Week 11. Subjects used topical antiseptic wash daily. Concomitant oral antibiotic use was allowed in Study HS-II. Both studies evaluated Hidradenitis Suppurativa Clinical Response (HiSCR) at Week 12. HiSCR was defined as at least a 50% reduction in total abscess and inflammatory nodule count with no increase in abscess count and no increase in draining fistula count relative to baseline (see Table 19). Reduction in HS-related skin pain was assessed using a Numeric Rating Scale in patients who entered the study with an initial baseline score of 3 or greater on a 11 point scale.

In both studies, a higher proportion of adalimumab- than placebo-treated subjects achieved HiSCR (see Table 19).

Table 19. Efficacy Results at 12 Weeks in Subjects with Moderate to Severe Hidradenitis Suppurativa
 | HS Study I |  | HS Study II [19.3% of subjects in Study HS-II continued baseline oral antibiotic therapy during the study.]
 | Placebo | Adalimumab 40 mg Weekly | Placebo | Adalimumab 40 mg Weekly
Hidradenitis Suppurativa Clinical Response (HiSCR) | N = 154 40 (26%) | N = 153 64 (42%) | N=163 45 (28%) | N=163 96 (59%)

In both studies, from Week 12 to Week 35 (Period B), subjects who had received adalimumab were re-randomized to 1 of 3 treatment groups (adalimumab 40 mg every week, adalimumab 40 mg every other week, or placebo). Subjects who had been randomized to placebo were assigned to receive adalimumab 40 mg every week (Study HS-I) or placebo (Study HS-II).

During Period B, flare of HS, defined as ≥25% increase from baseline in abscesses and inflammatory nodule counts and with a minimum of 2 additional lesions, was documented in 22 (22%) of the 100 subjects who were withdrawn from adalimumab treatment following the primary efficacy timepoint in two studies.

14.10 Adult Uveitis

The safety and efficacy of adalimumab were assessed in adult patients with non-infectious intermediate, posterior and panuveitis excluding patients with isolated anterior uveitis, in two randomized, double-masked, placebo-controlled studies (UV I and II). Patients received placebo or adalimumab at an initial dose of 80 mg followed by 40 mg every other week starting one week after the initial dose. The primary efficacy endpoint in both studies was ´time to treatment failure´.

Treatment failure was a multi-component outcome defined as the development of new inflammatory chorioretinal and/or inflammatory retinal vascular lesions, an increase in anterior chamber (AC) cell grade or vitreous haze (VH) grade or a decrease in best corrected visual acuity (BCVA).

Study UV I evaluated 217 patients with active uveitis while being treated with corticosteroids (oral prednisone at a dose of 10 to 60 mg/day). All patients received a standardized dose of prednisone 60 mg/day at study entry followed by a mandatory taper schedule, with complete corticosteroid discontinuation by Week 15.

Study UV II evaluated 226 patients with inactive uveitis while being treated with corticosteroids (oral prednisone 10 to 35 mg/day) at baseline to control their disease. Patients subsequently underwent a mandatory taper schedule, with complete corticosteroid discontinuation by Week 19.

Clinical Response

Results from both studies demonstrated statistically significant reduction of the risk of treatment failure in patients treated with adalimumab versus patients receiving placebo. In both studies, all components of the primary endpoint contributed cumulatively to the overall difference between adalimumab and placebo groups (Table 20).

Table 20. Time to Treatment Failure in Studies UV I and UV II
 | UV I |  |  | UV II
 | Placebo (N = 107) | adalimumab (N = 110) | HR [95% CI] [HR of adalimumab versus placebo from proportional hazards regression with treatment as factor.] | Placebo (N = 111) | adalimumab (N = 115) | HR [95% CI]
Failure [Treatment failure at or after Week 6 in Study UV I, or at or after Week 2 in Study UV II, was counted as event. Subjects who discontinued the study were censored at the time of dropping out.] n (%) | 84 (78.5) | 60 (54.5) | 0.50 [0.36, 0.70] | 61 (55.0) | 45 (39.1) | 0.57 [0.39, 0.84]
Median Time to Failure (Months) [95% CI] | 3.0 [2.7, 3.7] | 5.6 [3.9, 9.2] | N/A | 8.3 [4.8, 12.0] | NE [NE = not estimable. Fewer than half of at-risk subjects had an event.] | N/A

Figure 3: Kaplan-Meier Curves Summarizing Time to Treatment Failure on or after Week 6 (Study UV I) or Week 2 (Study UV II)

Study UV I

Study UV II

Note: P# = Placebo (Number of Events/Number at Risk); A# = adalimumab (Number of Events/Number at Risk).

15 REFERENCES

1. National Cancer Institute. Surveillance, Epidemiology, and End Results Database (SEER) Program. SEER Incidence Crude Rates, 17 Registries, 2000-2007.

16 HOW SUPPLIED/STORAGE AND HANDLING

AMJEVITA®(adalimumab-atto) injection is supplied as a preservative-free, sterile, clear, colorless to slightly yellow solution for subcutaneous administration. AMJEVITA is supplied in a single-dose prefilled syringe (PFS) or single-dose prefilled SureClick autoinjector (AI). The AMJEVITA prefilled syringe and prefilled SureClick autoinjector are not made with natural rubber latex.
The following packaging configurations are available.

Presentation | Number of Units/Pack | NDC number
20 mg/0.2 mL prefilled syringe with a fixed 29 gauge needle | 1 | 84612-399-01
40 mg/0.4 mL prefilled syringe with a fixed 29 gauge needle | 1 | 84612-479-01
40 mg/0.4 mL prefilled syringe with a fixed 29 gauge needle | 2 | 84612-479-02
80 mg/0.8 mL prefilled syringe with a fixed 29 gauge needle | 1 | 84612-480-01
40 mg/0.4 mL Prefilled SureClick Autoinjector | 1 | 84612-482-01
40 mg/0.4 mL Prefilled SureClick Autoinjector | 2 | 84612-482-02
80 mg/0.8 mL Prefilled SureClick Autoinjector | 1 | 84612-481-01
80 mg/0.8 mL Prefilled SureClick Autoinjector | 2 | 84612-481-02

Storage and Stability

Do not use beyond the expiration date on the container. AMJEVITA must be refrigerated at 36°F to 46°F (2°C to 8°C). DO NOT FREEZE. Do not use if frozen even if it has been thawed.

Store in original carton until time of administration to protect from light.

If needed, for example when traveling, AMJEVITA may be stored at room temperature up to a maximum of 77°F (25°C) for a period of up to 14 days, with protection from light. AMJEVITA should be discarded if not used within the 14-day period. Record the date when AMJEVITA is first removed from the refrigerator in the spaces provided on the carton.

Do not store AMJEVITA in extreme heat or cold.

17 PATIENT COUNSELING INFORMATION

Advise the patient or caregiver to read the FDA-approved patient labeling (Medication Guide and Instructions for Use).

Infections

Inform patients that AMJEVITA may lower the ability of their immune system to fight infections. Instruct patients of the importance of contacting their doctor if they develop any symptoms of infection, including tuberculosis, invasive fungal infections, and reactivation of hepatitis B virus infections [see Warnings and Precautions (5.1, 5.2, 5.4)] .

Malignancies

Counsel patients about the risk of malignancies while receiving AMJEVITA [see Warnings and Precautions (5.2)] .

Hypersensitivity Reactions

Advise patients to seek immediate medical attention if they experience any symptoms of severe hypersensitivity reactions.

Other Medical Conditions

Advise patients to report any signs of new or worsening medical conditions such as congestive heart failure, neurological disease, autoimmune disorders, or cytopenias. Advise patients to report any symptoms suggestive of a cytopenia such as bruising, bleeding, or persistent fever [see Warnings and Precautions (5.5, 5.6, 5.8, 5.9)] .

Instructions on Injection Technique

Inform patients that the first injection is to be performed under the supervision of a qualified health care professional. If a patient or caregiver is to administer AMJEVITA, instruct them in injection techniques and assess their ability to inject subcutaneously to ensure the proper administration of AMJEVITA [see Instructions for Use].

Instruct patients to dispose of their used needles and syringes or used prefilled autoinjector in a FDA-cleared sharps disposal container immediately after use. Instruct patients not to dispose of loose needles and syringes or prefilled autoinjector in their household trash.Instruct patients that if they do not have a FDA-cleared sharps disposal container, they may use a household container that is made of a heavy-duty plastic, can be closed with a tight-fitting and puncture-resistant lid without sharps being able to come out, upright and stable during use, leak-resistant, and properly labeled to warn of hazardous waste inside the container.

Instruct patients that when their sharps disposal container is almost full, they will need to follow their community guidelines for the correct way to dispose of their sharps disposal container.

Instruct patients that there may be state or local laws regarding disposal of used needles and syringes. Refer patients to the FDA's website at http://www.fda.gov/safesharpsdisposal for more information about safe sharps disposal, and for specific information about sharps disposal in the state that they live in.

Instruct patients not to dispose of their used sharps disposal container in their household trash unless their community guidelines permit this. Instruct patients not to recycle their used sharps disposal container.

AMJEVITA®(adalimumab-atto)

Manufactured for Nuvaila, Dublin, Ireland

Manufactured by: Amgen Inc., One Amgen Center Drive, Thousand Oaks, CA 91320-1799

U.S. License Number 1080

AMJEVITA®(adalimumab-atto) is a trademark owned or licensed by Amgen Inc., its subsidiaries, or affiliates.

All third party trademarks are the property of their respective owners.

© 2024 Amgen Inc. All rights reserved.

1xxxxxx-v1

MEDICATION GUIDE
AMJEVITA®(am-jeh-vee'-tah)
(adalimumab-atto)
injection, for subcutaneous use

Read the Medication Guide that comes with AMJEVITA before you start taking it and each time you get a refill. There may be new information. This Medication Guide does not take the place of talking with your doctor about your medical condition or treatment.

What is the most important information I should know about AMJEVITA?
AMJEVITA is a medicine that affects your immune system. AMJEVITA can lower the ability of your immune system to fight infections. Serious infections have happened in people taking adalimumab products. These serious infections include tuberculosis (TB) and infections caused by viruses, fungi or bacteria that have spread throughout the body. Some people have died from these infections.

- Your doctor should test you for TB before starting AMJEVITA.
- Your doctor should check you closely for signs and symptoms of TB during treatment with AMJEVITA.

You should not start taking AMJEVITA if you have any kind of infection unless your doctor says it is okay.
Before starting AMJEVITA, tell your doctor if you:

- think you have an infection or have symptoms of infection such as:

- fever, sweats, or chills
- muscle aches
- cough
- shortness of breath
- blood in phlegm

- warm, red, or painful skin or sores on your body
- diarrhea or stomach pain
- burning when you urinate or urinate more often than normal
- feeling very tired
- weight loss

- are being treated for an infection.
- get a lot of infections or have infections that keep coming back.
- have diabetes.
- have TB, or have been in close contact with someone with TB.
- were born in, lived in, or traveled to countries where there is more risk for getting TB. Ask your doctor if you are not sure.
- live or have lived in certain parts of the country (such as the Ohio and Mississippi River valleys) where there is an increased risk for getting certain kinds of fungal infections (histoplasmosis, coccidioidomycosis, or blastomycosis). These infections may happen or become more severe if you use AMJEVITA. Ask your doctor if you do not know if you have lived in an area where these infections are common.
- have or have had hepatitis B.
- use the medicine ORENCIA (abatacept), KINERET (anakinra), RITUXAN (rituximab), IMURAN (azathioprine), or PURINETHOL (6-mercaptopurine, 6-MP).
- are scheduled to have major surgery.

After starting AMJEVITA, call your doctor right awayif you have an infection, or any sign of an infection.
AMJEVITA can make you more likely to get infections or make any infection that you may have worse.
Cancer

- For children and adults taking Tumor Necrosis Factor (TNF)-blockers, including AMJEVITA, the chances of getting cancer may increase.
- There have been cases of unusual cancers in children, teenagers, and young adults using TNF-blockers.
- People with rheumatoid arthritis (RA), especially more serious RA, may have a higher chance for getting a kind of cancer called lymphoma.
- If you use TNF-blockers including AMJEVITA your chance of getting two types of skin cancer may increase (basal cell cancer and squamous cell cancer of the skin). These types of cancer are generally not life-threatening if treated. Tell your doctor if you have a bump or open sore that does not heal.
- Some people receiving TNF-blockers including AMJEVITA developed a rare type of cancer called hepatosplenic T-cell lymphoma. This type of cancer often results in death. Most of these people were male teenagers or young men. Also, most people were being treated for Crohn's disease or ulcerative colitis with another medicine called IMURAN (azathioprine) or PURINETHOL (6-mercaptopurine, 6-MP).

What is AMJEVITA?
AMJEVITA is a medicine called a Tumor Necrosis Factor (TNF)-blocker. AMJEVITA is used:

- To reduce the signs and symptoms of:
  - moderate to severe rheumatoid arthritis (RA) in adults.AMJEVITA can be used alone, with methotrexate, or with certain other medicines.
  - moderate to severe polyarticular juvenile idiopathic arthritis (JIA) in children2 years and older. AMJEVITA can be used alone or with methotrexate.
  - psoriatic arthritis (PsA) in adults.AMJEVITA can be used alone or with certain other medicines.
  - ankylosing spondylitis (AS) in adults.
  - moderate to severe hidradenitis suppurativa (HS) in adults.
- To treat moderate to severe Crohn's disease (CD) in adults and children 6 years of age and older.
- To treat moderate to severe ulcerative colitis (UC) in adults.It is not known if adalimumab products are effective in people who stopped responding to or could not tolerate TNF-blocker medicines.
- To treat moderate to severe chronic (lasting a long time) plaque psoriasis (Ps) in adultswho have the condition in many areas of their body and who may benefit from taking injections or pills (systemic therapy) or phototherapy (treatment using ultraviolet light alone or with pills).
- To treat non-infectious intermediate, posterior, and panuveitis in adults.

What should I tell my doctor before taking AMJEVITA?
AMJEVITA may not be right for you. Before starting AMJEVITA, tell your doctor about all of your medical conditions, including if you:

- have an infection. See " What is the most important information I should know about AMJEVITA?"
- have or have had cancer.
- have any numbness or tingling or have a disease that affects your nervous system such as multiple sclerosis or Guillain-Barré syndrome.
- have or had heart failure.
- have recently received or are scheduled to receive a vaccine. You may receive vaccines, except for live vaccines while using AMJEVITA. Children should be brought up to date with all vaccines before starting AMJEVITA.
- are allergic to AMJEVITA or to any of its ingredients. The AMJEVITA prefilled syringe and prefilled SureClick autoinjector are not made with natural rubber latex. See the end of this Medication Guide for a list of ingredients in AMJEVITA.
- are pregnant or plan to become pregnant, breastfeeding or plan to breastfeed. You and your doctor should decide if you should take AMJEVITA while you are pregnant or breastfeeding.
- have a baby and you were using AMJEVITA during your pregnancy. Tell your baby's doctor before your baby receives any vaccines.

Tell your doctor about all the medicines you take,including prescription and over-the-counter medicines, vitamins, and herbal supplements.
Especially tell your doctor if you use:

- ORENCIA (abatacept), KINERET (anakinra), REMICADE (infliximab), ENBREL (etanercept), CIMZIA (certolizumab pegol) or SIMPONI (golimumab), because you should not use AMJEVITA while you are also using one of these medicines.
- RITUXAN (rituximab). Your doctor may not want to give you AMJEVITA if you have received RITUXAN (rituximab) recently.
- IMURAN (azathioprine) or PURINETHOL (6-mercaptopurine, 6-MP).

Keep a list of your medicines with you to show your doctor and pharmacist each time you get a new medicine.

How should I take AMJEVITA?

- AMJEVITA is given by an injection under the skin. Your doctor will tell you how often to take an injection of AMJEVITA. This is based on your condition to be treated. Do not inject AMJEVITA more often than you were prescribed.
- See the Instructions for Useinside the carton for complete instructions for the right way to prepare and inject AMJEVITA.
- Make sure you have been shown how to inject AMJEVITA before you do it yourself. You can call your doctor or 1-800-77-AMGEN (1-800-772-6436) if you have any questions about giving yourself an injection. Someone you know can also help you with your injection after they have been shown how to prepare and inject AMJEVITA.
- Do nottry to inject AMJEVITA yourself until you have been shown the right way to give the injections. If your doctor decides that you or a caregiver may be able to give your injections of AMJEVITA at home, you should receive training on the right way to prepare and inject AMJEVITA.
- Do notmiss any doses of AMJEVITA unless your doctor says it is okay. If you forget to take AMJEVITA, inject a dose as soon as you remember. Then, take your next dose at your regular scheduled time. This will put you back on schedule. In case you are not sure when to inject AMJEVITA, call your doctor or pharmacist.
- If you take more AMJEVITA than you were told to take, call your doctor.

What are the possible side effects of AMJEVITA?
AMJEVITA can cause serious side effects, including:
See " What is the most important information I should know about AMJEVITA?"

- Serious Infections.
  Your doctor will examine you for TB and perform a test to see if you have TB. If your doctor feels that you are at risk for TB, you may be treated with medicine for TB before you begin treatment with AMJEVITA and during treatment with AMJEVITA. Even if your TB test is negative your doctor should carefully monitor you for TB infections while you are taking AMJEVITA. People who had a negative TB skin test before receiving adalimumab products have developed active TB. Tell your doctor if you have any of the following symptoms while taking or after taking AMJEVITA:

- cough that does not go away
- low grade fever

- weight loss
- loss of body fat and muscle (wasting)

- Hepatitis B infection in people who carry the virus in their blood.If you are a carrier of the hepatitis B virus (a virus that affects the liver), the virus can become active while you use AMJEVITA. Your doctor should do blood tests before you start treatment, while you are using AMJEVITA, and for several months after you stop treatment with AMJEVITA. Tell your doctor if you have any of the following symptoms of a possible hepatitis B infection:

- muscle aches
- feeling very tired
- dark urine
- skin or eyes look yellow
- little or no appetite
- vomiting

- clay-colored bowel movements
- fever
- chills
- stomach discomfort
- skin rash

- Allergic reactions.Allergic reactions can happen in people who use AMJEVITA. Call your doctor or get medical help right away if you have any of these symptoms of a serious allergic reaction:

- hives
- trouble breathing

- swelling of your face, eyes, lips or mouth

- Nervous system problems.Signs and symptoms of a nervous system problem include: numbness or tingling, problems with your vision, weakness in your arms or legs, and dizziness.
- Blood problems.Your body may not make enough of the blood cells that help fight infections or help to stop bleeding. Symptoms include a fever that does not go away, bruising or bleeding very easily, or looking very pale.
- New heart failure or worsening of heart failure you already have. Call your doctor right awayif you get new or worsening symptoms of heart failure while taking AMJEVITA, including:

- shortness of breath
- sudden weight gain

- swelling of your ankles or feet

- Immune reactions including a lupus-like syndrome.Symptoms include chest discomfort or pain that does not go away, shortness of breath, joint pain, or a rash on your cheeks or arms that gets worse in the sun. Symptoms may improve when you stop AMJEVITA.
- Liver problems.Liver problems can happen in people who use TNF-blocker medicines. These problems can lead to liver failure and death. Call your doctor right away if you have any of these symptoms:

- feel very tired
- poor appetite or vomiting

- skin or eyes look yellow
- pain on the right side of your stomach (abdomen)

- Psoriasis.Some people using adalimumab products had new psoriasis or worsening of psoriasis they already had. Tell your doctor if you develop red scaly patches or raised bumps that are filled with pus. Your doctor may decide to stop your treatment with AMJEVITA.

Call your doctor or get medical care right away if you develop any of the above symptoms. Your treatment with AMJEVITA may be stopped.
The most common side effects with AMJEVITA include:

- injection site reactions: redness, rash, swelling, itching, or bruising. These symptoms usually will go away within a few days. Call your doctor right away if you have pain, redness or swelling around the injection site that does not go away within a few days or gets worse.
- upper respiratory infections (including sinus infections).
- headaches.
- rash.

These are not all the possible side effects with AMJEVITA. Tell your doctor if you have any side effect that bothers you or that does not go away. Ask your doctor or pharmacist for more information.
Call your doctor for medical advice about side effects. You may report side effects to FDA at 1-800-FDA-1088.

How should I store AMJEVITA?

- Store AMJEVITA in the refrigerator at 36°F to 46°F (2°C to 8°C). Store AMJEVITA in the original carton until use to protect it from light.
- Do not freeze AMJEVITA.Do not use AMJEVITA if frozen, even if it has been thawed.
- Refrigerated AMJEVITA may be used until the expiration date printed on the AMJEVITA carton, dose tray, prefilled autoinjector or prefilled syringe. Do not use AMJEVITA after the expiration date.
- Record the date you first remove AMJEVITA from the refrigerator in the space provided on the carton.
- When traveling, AMJEVITA may be stored at room temperature up to 77°F (25°C) for up to 14 days.
- Throw away AMJEVITA if it has been kept at room temperature and not been used within 14 days.
- Do not store AMJEVITA in extreme heat or cold.
- Do not use a prefilled autoinjector or prefilled syringe if the liquid is cloudy, discolored, or has flakes or particles in it.
- Do not drop or crush the AMJEVITA syringe. The prefilled syringe is made of glass.

Keep AMJEVITA, injection supplies, and all other medicines out of the reach of children.

General information about the safe and effective use of AMJEVITA
Medicines are sometimes prescribed for purposes other than those listed in a Medication Guide. Do not use AMJEVITA for a condition for which it was not prescribed. Do not give AMJEVITA to other people, even if they have the same condition. It may harm them.
This Medication Guide summarizes the most important information about AMJEVITA. If you would like more information, talk with your doctor. You can ask your doctor or pharmacist for information about AMJEVITA that is written for health professionals.

What are the ingredients in AMJEVITA?
Active ingredient:adalimumab-atto
Inactive ingredients:glacial acetic acid, polysorbate 80, sucrose and Water for Injection. Sodium hydroxide is added as necessary to adjust the pH to 5.2.
AMJEVITA®(adalimumab-atto)
Manufactured for Nuvaila, Dublin, Ireland
Manufactured by: Amgen Inc., One Amgen Center Drive, Thousand Oaks, CA 91320-1799 U.S.A
U.S. License Number 1080
© 2024 Amgen Inc. All rights reserved.1xxxxxx – v1
For more information call 1-800-77-AMGEN (1-800-772-6436).

This Medication Guide has been approved by the U.S. Food and Drug Administration

Issued: 8/2024

INSTRUCTIONS FOR USE

AMJEVITA®(am-jeh-vee'-tah)
(adalimumab-atto)
injection, for subcutaneous use
20 mg/0.2 mL
40 mg/0.4 mL
80 mg/0.8 mL
single-dose prefilled syringe

This Instructions for Use contains information on how to inject AMJEVITA with a prefilled syringe.

If your healthcare provider decides that you or a caregiver may be able to give your injections of AMJEVITA at home, you should receive training on the right way to prepare and inject AMJEVITA. Do not try to inject yourself until you have been shown the right way to give the injections by your healthcare provider or nurse.

The medicine in the AMJEVITA prefilled syringe is for injection under the skin (subcutaneous injection). See the AMJEVITA Medication Guidefor information about AMJEVITA.

Getting to know your prefilled syringe

1. Important Information You Need to Know Before Injecting AMJEVITA

Dosing:

- AMJEVITA comes in 3 different doses: 20 mg/0.2 mL, 40 mg/0.4 mL, and 80 mg/0.8 mL. Check your prescription to make sure you have the correct dose.
- The color and look of the prefilled syringe will be different for each dose. The amount of medicine in the syringe will also be different for each dose.
- For example, it is okay for the 20 mg/0.2 mL dose to have a small amount of medicine and the 80 mg/0.8 mL to have a large amount of medicine. Check the illustrations below to see what your dose looks like in the syringe.

20 mg/0.2 mL

40 mg/0.4 mL

80 mg/0.8 mL

- It is important that you do not try to give the injection until you have fully read and understood this Instructions for Use.
- Do notuse the syringe if the carton is damaged or the seal is broken.
- Do notuse the syringe after the expiration date on the label.
- Do notshake the syringe.
- Do notremove the needle cap from the syringe until you are ready to inject.
- Do notuse the syringe if it has been frozen.
- Do notuse the syringe if it has been dropped on a hard surface. Part of the syringe may be broken even if you cannot see the break. Use a new syringe, and call 1-800-77-AMGEN (1-800-772-6436).
- The syringe is not made with natural rubber latex.

Important:Keep the syringe and sharps disposal container out of the sight and reach of children.

Frequently asked questions:
For additional information and answers to frequently asked questions, visit www.amjevita.com.

Where to get help:
If you want more information or help using AMJEVITA:

- Contact your healthcare provider,
- Visit www.amjevita.com, or
- Call 1-800-77-AMGEN (1-800-772-6436)

2. Storing and Preparing to Inject AMJEVITA

2a Refrigerate the syringe carton until you are ready to use it.

- Keep the syringe in the refrigerator between 36°F to 46°F (2°C to 8°C).
- Keep the syringe in the original carton to protect it from light or physical damage.
- Do notfreeze the syringe.
- Do notstore the syringe in extreme heat or cold. For example, avoid storing in your vehicle's glove box or trunk.

Important:Keep the syringe out of the sight and reach of children.

2b Grasp the syringe by the body and remove it from the carton.

- Do notgrab the finger grip, plunger rod, or the needle cap.
- Remove the number of syringes you need for your injection.
- Put any unused syringes back into the refrigerator.

WAIT

2c Wait 15 to 30 minutes for the syringe to reach room temperature.

- Let the syringe warm up naturally.
- Do notheat the syringe with hot water, a microwave, or direct sunlight.
- Do notshake the syringe at any time.
- Using the syringe at room temperature allows for a more comfortable injection .

2d You may keep AMJEVITA at room temperature for up to 14 days, if needed.

- For example, when you are traveling, you may keep AMJEVITA at room temperature.
  - Keep it at room temperature between 68°F to 77°F (20°C to 25°C).
  - Do notput it back in the refrigerator.
  - Record the date you removed it from the refrigerator and use it within 14days.

Important:Place the syringe in a sharps disposal container if it has reached room temperature and has not been used within 14days.

2e Gather and place the following items for your injection on a clean, flat, and well-lit surface:

- AMJEVITA syringe (room temperature)
- Sharps disposal container [see Disposing of AMJEVITA and Checking the Injection Site]
- Alcohol wipe
- Adhesive bandage
- Cotton ball or gauze pad

3. Getting Ready for Your Injection

3a Inspect the medicine. It should be clear and colorless to pale yellow.

- It is okay to see air bubbles in the syringe.
- Do notuse AMJEVITA if the medicine is cloudy, discolored, or has flakes or particles.

Important:If the medicine is cloudy, discolored, or has flakes or particles, or if the syringe is damaged or expired, call 1-800-77-AMGEN (1-800-772-6436).

3b Check the expiration date (Exp.) and inspect the syringe for damage.

- Do notuse the syringe if the expiration date has passed.
- Do notuse the syringe if:
  - the needle cap is missing or loose.
  - it has cracks or broken parts.
  - it has been dropped on a hard surface.
- Make sure you have the right medicine and dose.

3c Inject into 1 of these locations.

- Inject into the front of your thigh or stomach (except for 2 inches around your belly button).
- Choose a different site for each injection.

Important:Avoid areas with scars or stretch marks, or where the skin is tender, bruised, red, or hard.

3d Wash hands thoroughly with soap and water.

3e Clean the injection site with an alcohol wipe.

- Let the skin dry on its own.
- Do nottouch this area again before injecting.

4. Injecting AMJEVITA

Important:Only remove the needle cap when you can inject right away (within 5 minutes) because the medicine can dry out. Do notrecap.

4a Pull the needle cap straight off while holding the syringe body.

- Do nottwist or bend the needle cap.
- Neverput the needle cap back on. It may damage the needle.
- Do notlet anything touch the needle after you remove the needle cap.
- Do notplace the uncapped syringe on any surface after you remove the needle cap.
- Do nottry to push air bubbles out of the syringe. It is okay to see air bubbles.
- It is normal to see a drop of medicine come out of the needle.

Important:Never put the needle cap back on to avoid accidental needlestick injury.

4b Place the needle cap in the sharps disposal container.

4c Pinch the skin around the injection site before injection.

- Pinch the skin between the thumb and pointer (index) finger to create a bump for the injection.
- If possible, the bump should be about 2 inches wide.

Important:Continue to pinch the skin until the injection is complete.

INSERT

4d Insert the needle into the pinched skin at a 45-degree angle.

- Do notplace your finger on the plunger rod while inserting the needle, as this may result in lost medicine.

INJECT

4e Slowly press the plunger rod all the way down until it reaches the bottom of the syringe to inject the medicine.

- Do notpull back on the plunger rod at any time.
- Do notremove the syringe until all of the medicine has been injected.

5. Disposing of AMJEVITA and Checking the Injection Site

Important:Never put the needle cap back on.

5a Place the used syringe in an FDA-cleared sharps disposal container right away after use.

Important:Do not throw away the syringe in your household trash.

- Do notreuse the syringe.

5b Check the injection site.

- Do notrub the injection site.
- If there is blood, press a cotton ball or gauze pad on your injection site. Apply an adhesive bandage if necessary.

Additional information about your sharps disposal container

If you do not have an FDA-cleared sharps disposal container, you may use a household container that is:

- made of a heavy-duty plastic,
- can be closed with a tight-fitting, puncture-resistant lid, without sharps being able to come out,
- upright and stable during use,
- leak-resistant, and
- properly labeled to warn of hazardous waste inside the container.

Disposing of sharps disposal containers:

When your sharps disposal container is almost full, you will need to follow your community guidelines for the right way to dispose of your sharps disposal container.

There may be state or local laws about how you should throw away used needles and syringes.

For more information about safe sharps disposal, and for specific information about sharps disposal in the state that you live in, go to the FDA's website at:

http://www.fda.gov/safesharpsdisposal

Do not dispose of your used sharps disposal container in your household trashunless your community guidelines permit this.

Do not recycle your used sharps disposal container.

For more information or help call 1-800-77-AMGEN (1-800-772-6436).

This Instructions for Use has been approved by the U.S. Food and Drug Administration.

AMJEVITA®(adalimumab-atto)

Manufactured for Nuvaila, Dublin, Ireland

Manufactured by: Amgen Inc., One Amgen Center Drive, Thousand Oaks, California 91320-1799
US License Number 1080
©2024 Amgen Inc. All rights reserved.

nnnnnnnnnn
Issued: 08/2024
v1

INSTRUCTIONS FOR USE

AMJEVITA®(am-jeh-vee'-tah)
(adalimumab-atto)
injection, for subcutaneous use
40 mg/0.4 mL
single-dose prefilled SureClick®autoinjector

This Instructions for Use contains information on how to inject AMJEVITA with a SureClick autoinjector.

If your healthcare provider decides that you or a caregiver may be able to give your injections of AMJEVITA at home, you should receive training on the right way to prepare and inject AMJEVITA. Do not try to inject yourself until you have been shown the right way to give the injections by your healthcare provider or nurse.

The medicine in the AMJEVITA autoinjector is for injection under the skin (subcutaneous injection). See the AMJEVITA Medication Guidefor information about AMJEVITA.

Getting to know your prefilled autoinjector

1. Important Information You Need to Know Before Injecting AMJEVITA

- It is important that you do not try to give the injection until you have fully read and understood this Instructions for Use.
- Do notuse the autoinjector if the carton is damaged or the seal is broken.
- Do notuse the autoinjector after the expiration date on the label.
- Do notshake the autoinjector.
- Do notremove the yellow cap from the autoinjector until you are ready to inject.
- Do notuse the autoinjector if it has been frozen.
- Do notuse the autoinjector if it has been dropped on a hard surface. Part of the autoinjector may be broken even if you cannot see the break. Use a new autoinjector, and call 1-800-77-AMGEN (1-800-772-6436).
- The autoinjector is not made with natural rubber latex.

Important:Keep the autoinjector and sharps disposal container out of the sight and reach of children.

Frequently asked questions:

For additional information and answers to frequently asked questions, visit www.amjevita.com.

Where to get help:

If you want more information or help using AMJEVITA:

- Contact your healthcare provider,
- Visit www.amjevita.com, or
- Call 1-800-77-AMGEN (1-800-772-6436)

2. Storing and Preparing to Inject AMJEVITA

2a Refrigerate the autoinjector carton until you are ready to use it.

- Keep the autoinjector in the refrigerator between 36°F to 46°F (2°C to 8°C).
- Keep the autoinjector in the original carton to protect it from light or physical damage.
- Do notfreeze the autoinjector.
- Do notstore the autoinjector in extreme heat or cold. For example, avoid storing in your vehicle's glove box or trunk.

Important:Keep the autoinjector out of the sight and reach of children.

WAIT

2b Wait 15 to 30 minutes for the autoinjector to reach room temperature.

- Remove the number of autoinjectors you need for your injection and put any unused autoinjectors back into the refrigerator.
- Let the autoinjector warm up naturally.
- Do notheat the autoinjector with hot water, a microwave, or direct sunlight.
- Do notshake the autoinjector at any time.
- Using the autoinjector at room temperature makes sure the full dose is delivered and allows for a more comfortable injection.

2c You may keep AMJEVITA at room temperature for up to 14days, if needed.

- For example, when you are traveling, you may keep AMJEVITA at room temperature.
  - Keep it at room temperature between 68°F to 77°F (20°C to 25°C).
  - Do notput it back in the refrigerator.
  - Record the date you removed it from the refrigerator and use it within 14days.

Important:Place the autoinjector in a sharps disposal container if it has reached room temperature and has not been used within 14days.

2d Inspect the medicine. It should be clear and colorless to pale yellow.

- It is okay to see air bubbles in the autoinjector.
- Do notuse AMJEVITA if the medicine is cloudy, discolored, or has flakes or particles.

Important:If the medicine is cloudy, discolored, or has flakes or particles, or if the autoinjector is damaged or expired, call 1-800-77-AMGEN (1-800-772-6436).

2e Check the expiration date (Exp.) and inspect the autoinjector for damage.

- Do notuse the autoinjector if the expiration date has passed.
- Do notuse the autoinjector if:
  - the yellow cap is missing or loose.
  - it has cracks or broken parts.
  - it has been dropped on a hard surface.
- Make sure you have the right medicine and dose.

3. Getting Ready for Your Injection

3a Gather and place the following items for your injection on a clean, flat, and well-lit surface:

- AMJEVITA autoinjector (room temperature)
- Sharps disposal container [see Disposing of AMJEVITA and Checking the Injection Site]
- Alcohol wipe
- Adhesive bandage
- Cotton ball or gauze pad

3b Inject into 1 of these locations.

- Inject into the front of your thigh or stomach (except for 2 inches around your belly button).
- Choose a different site for each injection.

Important:Avoid areas with scars or stretch marks, or where the skin is tender, bruised, red, or hard.

3c Wash hands thoroughly with soap and water.

3d Clean the injection site with an alcohol wipe.

- Let the skin dry on its own.
- Do nottouch this area again before injecting.

4. Injecting AMJEVITA

Important:Only remove the yellow cap when you can inject right away (within 5 minutes) because the medicine can dry out. Do notrecap.

4a Grasp the autoinjector so you can see the window. Pull the yellow cap straight off. You may need to pull hard.

- Do nottwist, bend or wiggle the yellow cap to pull it off.
- Neverput the yellow cap back on. It may damage the needle.
- Do notput your finger inside the cream safety guard.
- It is normal to see a drop of medicine at the end of the needle or cream safety guard.

4b Pinch the skin to create a firm surface at the injection site. Place the cream safety guard straight against the pinched skin.

- Keep the skin pincheduntil the injection is finished.
- Make sure you can see the window.
- Make sure the autoinjector is positioned straight on the injection site (at a 90-degree angle).

PUSH
and hold against skin

4c Firmly push the autoinjector down until the cream safety guard stops moving. Hold the autoinjector down, do not lift.

- The cream safety guard pushes in and unlocks the light blue start button.

PRESS
light blue start button

4d Keep pushing the autoinjector down and press the light blue start button to start the injection.

- You may hear or feel a click.
- The window starts to turn yellow.
- It is okay to let go of the light blue start button.

WATCH and CONFIRM
that the window turns fully yellow

4e Keep pushing the autoinjector down. When the window is fully yellow, the injection is complete.

- The injection may take up to 10seconds to complete.
- You may hear or feel a click.
- Lift the autoinjector away from your skin.
- The cream safety guard locks around the needle.

Important:If the window has not turned fully yellow, or it looks like the medicine is still coming out, you have not received a full dose. Call your healthcare provider right away.

5. Disposing of AMJEVITA and Checking the Injection Site

5a Place the used autoinjector and yellow cap in an FDA-cleared sharps disposal container right away after use.

Important: Do not throw away the autoinjector in your household trash.

- Do notreuse the autoinjector.
- Do nottouch the cream safety guard.

5b Check the injection site.

- Do notrub the injection site.
- If there is blood, press a cotton ball or gauze pad on your injection site. Apply an adhesive bandage if necessary.

Additional information about your sharps disposal container

If you do not have an FDA-cleared sharps disposal container, you may use a household container that is:

- made of a heavy-duty plastic,
- can be closed with a tight-fitting, puncture-resistant lid, without sharps being able to come out,
- upright and stable during use,
- leak-resistant, and
- properly labeled to warn of hazardous waste inside the container.

Disposing of sharps disposal containers:

When your sharps disposal container is almost full, you will need to follow your community guidelines for the right way to dispose of your sharps disposal container.

There may be state or local laws about how you should throw away used needles and syringes.

For more information about safe sharps disposal, and for specific information about sharps disposal in the state that you live in, go to the FDA's website at:
http://www.fda.gov/safesharpsdisposal

Do not dispose of your used sharps disposal container in your household trashunless your community guidelines permit this.

Do not recycle your used sharps disposal container.

For more information or help call 1-800-77-AMGEN (1-800-772-6436).

This Instructions for Use has been approved by the U.S. Food and Drug Administration.

AMJEVITA®(adalimumab-atto)

Manufactured for Nuvaila, Dublin, Ireland

Manufactured by: Amgen Inc., One Amgen Center Drive, Thousand Oaks, California 91320-1799
US License Number 1080
©2024 Amgen Inc. All rights reserved.
nnnnnnnnnn
Issued: 08/2024
v1

INSTRUCTIONS FOR USE

AMJEVITA®(am-jeh-vee'-tah)
(adalimumab-atto)
injection, for subcutaneous use
80 mg/0.8 mL
single-dose prefilled SureClick®autoinjector

This Instructions for Use contains information on how to inject AMJEVITA with a SureClick autoinjector.

If your healthcare provider decides that you or a caregiver may be able to give your injections of AMJEVITA at home, you should receive training on the right way to prepare and inject AMJEVITA. Do not try to inject yourself until you have been shown the right way to give the injections by your healthcare provider or nurse.

The medicine in the AMJEVITA autoinjector is for injection under the skin (subcutaneous injection). See the AMJEVITA Medication Guidefor information about AMJEVITA.

Getting to know your prefilled autoinjector

1. Important Information You Need to Know Before Injecting AMJEVITA

- It is important that you do not try to give the injection until you have fully read and understood this Instructions for Use.
- Do notuse the autoinjector if the carton is damaged or the seal is broken.
- Do notuse the autoinjector after the expiration date on the label.
- Do notshake the autoinjector.
- Do notremove the yellow cap from the autoinjector until you are ready to inject.
- Do notuse the autoinjector if it has been frozen.
- Do notuse the autoinjector if it has been dropped on a hard surface. Part of the autoinjector may be broken even if you cannot see the break. Use a new autoinjector, and call 1-800-77-AMGEN (1-800-772-6436).
- The autoinjector is not made with natural rubber latex.

Important:Keep the autoinjector and sharps disposal container out of the sight and reach of children.

Frequently asked questions:

For additional information and answers to frequently asked questions, visit www.amjevita.com.

Where to get help:

If you want more information or help using AMJEVITA:

- Contact your healthcare provider,
- Visit www.amjevita.com, or
- Call 1-800-77-AMGEN (1-800-772-6436)

2. Storing and Preparing to Inject AMJEVITA

2a Refrigerate the autoinjector carton until you are ready to use it.

- Keep the autoinjector in the refrigerator between 36°F to 46°F (2°C to 8°C).
- Keep the autoinjector in the original carton to protect it from light or physical damage.
- Do notfreeze the autoinjector.
- Do notstore the autoinjector in extreme heat or cold. For example, avoid storing in your vehicle's glove box or trunk.

Important:Keep the autoinjector out of the sight and reach of children.

WAIT

2b Wait 15 to 30 minutes for the autoinjector to reach room temperature.

- Remove the number of autoinjectors you need for your injection and put any unused autoinjectors back into the refrigerator.
- Let the autoinjector warm up naturally.
- Do notheat the autoinjector with hot water, a microwave, or direct sunlight.
- Do notshake the autoinjector at any time.
- Using the autoinjector at room temperature makes sure the full dose is delivered and allows for a more comfortable injection.

2c You may keep AMJEVITA at room temperature for up to 14days, if needed.

- For example, when you are traveling, you may keep AMJEVITA at room temperature.
  - Keep it at room temperature between 68°F to 77°F (20°C to 25°C).
  - Do notput it back in the refrigerator.
  - Record the date you removed it from the refrigerator and use it within 14days.

Important:Place the autoinjector in a sharps disposal container if it has reached room temperature and has not been used within 14days.

2d Inspect the medicine. It should be clear and colorless to pale yellow.

- It is okay to see air bubbles in the autoinjector.
- Do notuse AMJEVITA if the medicine is cloudy, discolored, or has flakes or particles.

Important:If the medicine is cloudy, discolored, or has flakes or particles, or if the autoinjector is damaged or expired, call 1-800-77-AMGEN (1-800-772-6436).

2e Check the expiration date (Exp.) and inspect the autoinjector for damage.

- Do notuse the autoinjector if the expiration date has passed.
- Do notuse the autoinjector if:
  - the yellow cap is missing or loose.
  - it has cracks or broken parts.
  - it has been dropped on a hard surface.
- Make sure you have the right medicine and dose.

3. Getting Ready for Your Injection

3a Gather and place the following items for your injection on a clean, flat, and well-lit surface:

- AMJEVITA autoinjector (room temperature)
- Sharps disposal container [see Disposing of AMJEVITA and Checking the Injection Site]
- Alcohol wipe
- Adhesive bandage
- Cotton ball or gauze pad

3b Inject into 1 of these locations.

- Inject into the front of your thigh or stomach (except for 2 inches around your belly button).
- Choose a different site for each injection.

Important:Avoid areas with scars or stretch marks, or where the skin is tender, bruised, red, or hard.

3c Wash hands thoroughly with soap and water.

3d Clean the injection site with an alcohol wipe.

- Let the skin dry on its own.
- Do nottouch this area again before injecting.

4. Injecting AMJEVITA

Important:Only remove the yellow cap when you can inject right away (within 5 minutes) because the medicine can dry out. Do notrecap.

4a Grasp the autoinjector so you can see the window. Pull the yellow cap straight off. You may need to pull hard.

- Do nottwist, bend or wiggle the yellow cap to pull it off.
- Neverput the yellow cap back on. It may damage the needle.
- Do notput your finger inside the cream safety guard.
- It is normal to see a drop of medicine at the end of the needle or cream safety guard.

4b Pinch the skin to create a firm surface at the injection site. Place the cream safety guard straight against the pinched skin.

- Keep the skin pincheduntil the injection is finished.
- Make sure you can see the window.
- Make sure the autoinjector is positioned straight on the injection site (at a 90-degree angle).

PUSH
and hold against skin

4c Firmly push the autoinjector down until the cream safety guard stops moving. Hold the autoinjector down, do not lift.

- The cream safety guard pushes in and unlocks the light blue start button.

PRESS
light blue start button

4d Keep pushing the autoinjector down and press the light blue start button to start the injection.

- You may hear or feel a click.
- The window starts to turn yellow.
- It is okay to let go of the light blue start button.

WATCH and CONFIRM
that the window turns fully yellow

4e Keep pushing the autoinjector down. When the window is fully yellow, the injection is complete.

- The injection may take up to 15seconds to complete.
- You may hear or feel a click.
- Lift the autoinjector away from your skin.
- The cream safety guard locks around the needle.

Important:If the window has not turned fully yellow, or it looks like the medicine is still coming out, you have not received a full dose. Call your healthcare provider right away.

5. Disposing of AMJEVITA and Checking the Injection Site

5a Place the used autoinjector and yellow cap in an FDA-cleared sharps disposal container right away after use.

Important: Do not throw away the autoinjector in your household trash.

- Do notreuse the autoinjector.
- Do nottouch the cream safety guard.

5b Check the injection site.

- Do notrub the injection site.
- If there is blood, press a cotton ball or gauze pad on your injection site. Apply an adhesive bandage if necessary.

Additional information about your sharps disposal container

If you do not have an FDA-cleared sharps disposal container, you may use a household container that is:

- made of a heavy-duty plastic,
- can be closed with a tight-fitting, puncture-resistant lid, without sharps being able to come out,
- upright and stable during use,
- leak-resistant, and
- properly labeled to warn of hazardous waste inside the container.

Disposing of sharps disposal containers:

When your sharps disposal container is almost full, you will need to follow your community guidelines for the right way to dispose of your sharps disposal container.

There may be state or local laws about how you should throw away used needles and syringes.

For more information about safe sharps disposal, and for specific information about sharps disposal in the state that you live in, go to the FDA's website at:
http://www.fda.gov/safesharpsdisposal

Do not dispose of your used sharps disposal container in your household trashunless your community guidelines permit this.

Do not recycle your used sharps disposal container.

For more information or help call 1-800-77-AMGEN (1-800-772-6436).

This Instructions for Use has been approved by the U.S. Food and Drug Administration.

AMJEVITA®(adalimumab-atto)

Manufactured for Nuvaila, Dublin, Ireland

Manufactured by: Amgen Inc., One Amgen Center Drive, Thousand Oaks, California 91320-1799
US License Number 1080
©2024 Amgen Inc. All rights reserved.
nnnnnnnnnn
Issued: 08/2024
v1

PRINCIPAL DISPLAY PANEL - 20 mg/0.2 mL Syringe Carton

AMJEVITA®
(adalimumab-atto)
Injection

NDC 84612-399-01

20 mg/0.2 mL

For Subcutaneous Use Only

Sterile Solution – No Preservative

Store refrigerated at 2°C to 8°C (36°F to 46°F).
Do not Freeze. Do not re-use. Do not Shake.
Protect from light.
(see side panel for additional storage information)
Keep out of the sight and reach of children.

ATTENTION: Enclosed Medication Guide is required
for each patient.

Manufactured for:
nuvaila

Rx Only

Do not use
if carton seal is broken

Not made with
natural rubber latex

20 mg/
0.2 mL

1 Single-dose
Prefilled Syringe

For Use in Pediatric Patients
15 kg to < 30 kg

Refrigerate
until ready
to use

CAUTION, Consult
Accompanying Documents

PRINCIPAL DISPLAY PANEL - 40 mg/0.4 mL Syringe Carton

AMJEVITA®
(adalimumab-atto)
Injection

NDC 84612-479-02

40 mg/0.4 mL

For Subcutaneous Use Only

Sterile Solution – No Preservative

Store refrigerated at 2°C to 8°C (36°F to 46°F).
Do not Freeze. Do not re-use. Do not Shake.
Protect from light.
(see side panel for additional storage information)
Keep out of the sight and reach of children.

ATTENTION: Enclosed Medication Guide is required
for each patient.

Manufactured for:
nuvaila

Rx Only

Do not use
if carton seal is broken

Not made with
natural rubber latex

40 mg/
0.4 mL

2 Single-dose
Prefilled Syringes

Refrigerate
until ready
to use

CAUTION, Consult
Accompanying Documents

PRINCIPAL DISPLAY PANEL - 40 mg/0.4 mL Autoinjector Carton

AMJEVITA®
(adalimumab-atto)
Injection

NDC 84612-482-02

40 mg/0.4 mL

For Subcutaneous Use Only

Sterile Solution – No Preservative

Store refrigerated at 2°C to 8°C (36°F to 46°F).
Do not Freeze. Do not re-use.
Do not Shake. Protect from light.
(see side panel for additional storage information)

Keep out of the sight and reach of children.

ATTENTION: Enclosed Medication Guide is
required for each patient.

Manufactured for:
nuvaila

Rx Only

Not made with
natural rubber latex

40 mg/
0.4 mL

2
Single-dose Prefilled
SureClick®Autoinjectors

Refrigerate
until ready
to use

CAUTION, Consult
Accompanying Documents

PRINCIPAL DISPLAY PANEL - 80 mg/0.8 mL Autoinjector Carton

AMJEVITA®
(adalimumab-atto)
Injection

NDC 84612-481-02

80 mg/0.8 mL

For Subcutaneous Use Only

Sterile Solution – No Preservative

Store refrigerated at 2°C to 8°C (36°F to 46°F).
Do not Freeze. Do not re-use.
Do not Shake. Protect from light.
(see side panel for additional storage information)

Keep out of the sight and reach of children.

ATTENTION: Enclosed Medication Guide is
required for each patient.

Manufactured for:
nuvaila

Rx Only

Not made with
natural rubber latex

80 mg/
0.8 mL

2
Single-dose Prefilled
SureClick®Autoinjectors

Refrigerate
until ready
to use

CAUTION, Consult
Accompanying Documents